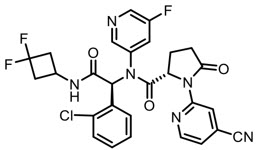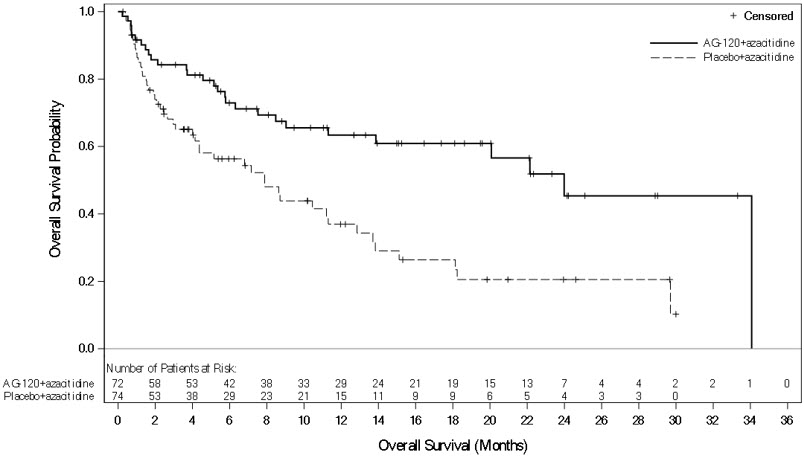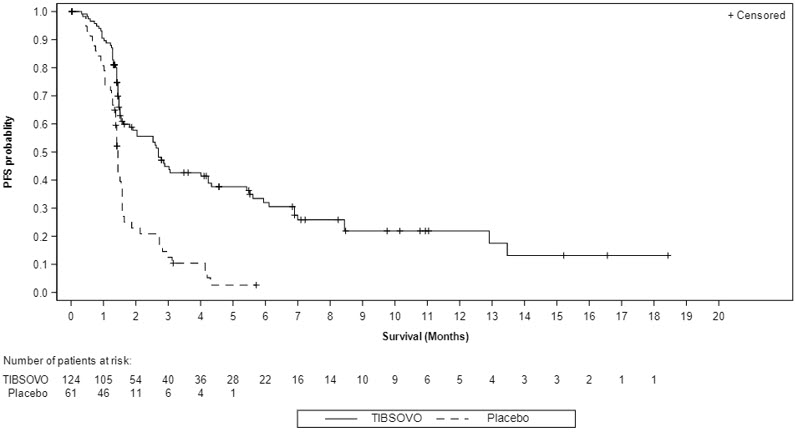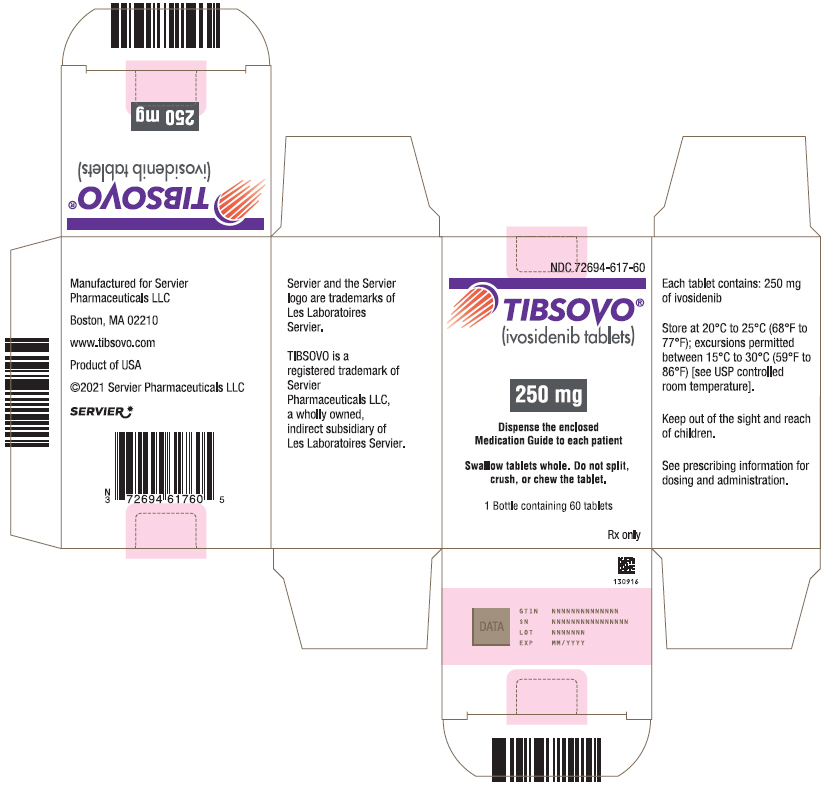 DRUG LABEL: TIBSOVO
NDC: 72694-617 | Form: TABLET, FILM COATED
Manufacturer: Servier Pharmaceutical LLC
Category: prescription | Type: HUMAN PRESCRIPTION DRUG LABEL
Date: 20251222

ACTIVE INGREDIENTS: ivosidenib 250 mg/1 1
INACTIVE INGREDIENTS: Silicon dioxide; Croscarmellose sodium; HYPROMELLOSE ACETATE SUCCINATE 06081224 (3 MPA.S); Magnesium stearate; Microcrystalline cellulose; sodium lauryl sulfate; FD&C BLUE NO. 2; Hypromellose, unspecified; Lactose Monohydrate; Titanium Dioxide; Triacetin

HIGHLIGHTS OF PRESCRIBING INFORMATION

These highlights do not include all the information needed to use TIBSOVO safely and effectively. See full prescribing information for TIBSOVO.
TIBSOVO® (ivosidenib tablets), for oral use
Initial U.S. Approval: 2018

WARNING: DIFFERENTIATION SYNDROME IN AML AND MDS

See full prescribing information for complete boxed warning.

Patients treated with TIBSOVO have experienced symptoms of differentiation syndrome, which can be fatal. If differentiation syndrome is suspected, initiate corticosteroid therapy and hemodynamic monitoring until symptom resolution (5.1, 6.1).

RECENT MAJOR CHANGES

Indications and Usage, Relapsed or Refractory MDS (1.3) | 10/2023
Dosage and Administration, Patient Selection (2.1) | 10/2023
Dosage and Administration, Recommended Dosage (2.2) | 10/2023

1 INDICATIONS AND USAGE

TIBSOVO is an isocitrate dehydrogenase-1 (IDH1) inhibitor indicated for patients with a susceptible IDH1 mutation as detected by an FDA-approved test with:

Newly Diagnosed Acute Myeloid Leukemia (AML)

- In combination with azacitidine or as monotherapy for the treatment of newly diagnosed AML in adults 75 years or older, or who have comorbidities that preclude use of intensive induction chemotherapy (1.1).

Relapsed or refractory AML

- For the treatment of adult patients with relapsed or refractory AML (1.2).

Relapsed or refractory Myelodysplastic Syndromes (MDS)

- For the treatment of adult patients with relapsed or refractory myelodysplastic syndromes (1.3).

Locally Advanced or Metastatic Cholangiocarcinoma

- For the treatment of adult patients with locally advanced or metastatic cholangiocarcinoma who have been previously treated (1.4).

2 DOSAGE AND ADMINISTRATION

500 mg orally once daily with or without food until disease progression or unacceptable toxicity (2.2). Avoid a high-fat meal.

3 DOSAGE FORMS AND STRENGTHS

Tablets: 250 mg (3).

4 CONTRAINDICATIONS

None (4).

5 WARNINGS AND PRECAUTIONS

- QTc Interval Prolongation: Monitor electrocardiograms and electrolytes. If QTc interval prolongation occurs, dose reduce or withhold, then resume dose or permanently discontinue TIBSOVO (2.3, 5.2).
- Guillain-Barré Syndrome: Monitor patients for signs and symptoms of new motor and/or sensory findings. Permanently discontinue TIBSOVO in patients who are diagnosed with Guillain-Barré syndrome (2.3, 5.3).

6 ADVERSE REACTIONS

The most common adverse reactions including laboratory abnormalities (≥ 25%) in patients with AML are leukocytes decreased, diarrhea, hemoglobin decreased, platelets decreased, glucose increased, fatigue, alkaline phosphatase increased, edema, potassium decreased, nausea, vomiting, phosphate decreased, decreased appetite, sodium decreased, leukocytosis, magnesium decreased, aspartate aminotransferase increased, arthralgia, dyspnea, uric acid increased, abdominal pain, creatinine increased, mucositis, rash, electrocardiogram QT prolonged, differentiation syndrome, calcium decreased, neutrophils decreased, and myalgia (6.1).

The most common adverse reactions including laboratory abnormalities (≥25%) in patients with relapsed or refractory MDS are creatinine increased, hemoglobin decrease, arthralgia, albumin decreased, aspartate aminotransferase increased, fatigue, diarrhea, cough, sodium decreased, mucositis, decreased appetite, myalgia, phosphate decreased, pruritus, and rash (6.1).

The most common adverse reactions (≥15%) in patients with cholangiocarcinoma are fatigue, nausea, abdominal pain, diarrhea, cough, decreased appetite, ascites, vomiting, anemia, and rash (6.1).

The most common laboratory abnormalities (≥10%) in patients with cholangiocarcinoma are hemoglobin decreased, aspartate aminotransferase increased, and bilirubin increased (6.1).

To report SUSPECTED ADVERSE REACTIONS, contact Servier Pharmaceuticals at 1-800-807-6124 or FDA at 1-800-FDA-1088 or www.fda.gov/medwatch.

7 DRUG INTERACTIONS

- Strong or Moderate CYP3A4 Inhibitors: Reduce TIBSOVO dose with strong CYP3A4 inhibitors. Monitor patients for increased risk of QTc interval prolongation (2.4, 5.2, 7.1, 12.3).
- Strong CYP3A4 Inducers: Avoid concomitant use with TIBSOVO (7.1, 12.3).
- Sensitive CYP3A4 substrates: Avoid concomitant use with TIBSOVO (7.2, 12.3).
- QTc Prolonging Drugs: Avoid concomitant use with TIBSOVO. If co-administration is unavoidable, monitor patients for increased risk of QTc interval prolongation (5.2, 7.1).

8 USE IN SPECIFIC POPULATIONS

Lactation: Advise women not to breastfeed (8.2).

FULL PRESCRIBING INFORMATION

WARNING: DIFFERENTIATION SYNDROME IN AML AND MDS

Patients treated with TIBSOVO have experienced symptoms of differentiation syndrome, which can be fatal. Symptoms may include fever, dyspnea, hypoxia, pulmonary infiltrates, pleural or pericardial effusions, rapid weight gain or peripheral edema, hypotension, and hepatic, renal, or multi-organ dysfunction. If differentiation syndrome is suspected, initiate corticosteroid therapy and hemodynamic monitoring until symptom resolution [see Warnings and Precautions (5.1) and Adverse Reactions (6.1)].

1 INDICATIONS AND USAGE

1.1 Newly Diagnosed Acute Myeloid Leukemia

TIBSOVO is indicated in combination with azacitidine or as monotherapy for the treatment of newly diagnosed acute myeloid leukemia (AML) with a susceptible isocitrate dehydrogenase-1 (IDH1) mutation as detected by an FDA-approved test in adults 75 years or older, or who have comorbidities that preclude use of intensive induction chemotherapy [see Dosage and Administration (2.1), Clinical Pharmacology (12.1) and Clinical Studies (14.1)].

1.2 Relapsed or Refractory Acute Myeloid Leukemia

TIBSOVO is indicated for the treatment of adult patients with relapsed or refractory acute myeloid leukemia (AML) with a susceptible isocitrate dehydrogenase-1 (IDH1) mutation as detected by an FDA-approved test [see Dosage and Administration (2.1), Clinical Pharmacology (12.1) and Clinical Studies (14.2)].

1.3 Relapsed or Refractory Myelodysplastic Syndromes

TIBSOVO is indicated for the treatment of adult patients with relapsed or refractory myelodysplastic syndromes (MDS) with a susceptible isocitrate dehydrogenase-1 (IDH1) mutation as detected by an FDA-approved test [see Dosage and Administration (2.1), Clinical Pharmacology (12.1) and Clinical Studies (14.3)].

1.4 Locally Advanced or Metastatic Cholangiocarcinoma

TIBSOVO is indicated for the treatment of adult patients with previously treated, locally advanced or metastatic cholangiocarcinoma with an isocitrate dehydrogenase-1 (IDH1) mutation as detected by an FDA-approved test [see Dosage and Administration (2.1), Clinical Pharmacology (12.1), and Clinical Studies (14.4)].

2 DOSAGE AND ADMINISTRATION

2.1 Patient Selection

Select patients for treatment with TIBSOVO based on the presence of IDH1 mutations [see Clinical Studies (14.1, 14.2, 14.3, 14.4)].

Information on FDA-approved tests for the detection of IDH1 mutations in AML, MDS, and cholangiocarcinoma is available at http://www.fda.gov/CompanionDiagnostics.

2.2 Recommended Dosage

The recommended dosage of TIBSOVO is 500 mg taken orally once daily until disease progression or unacceptable toxicity [see Clinical Studies (14.1, 14.2, 14.3, 14.4)].

For patients with AML or MDS without disease progression or unacceptable toxicity, continue TIBSOVO for a minimum of 6 months to allow time for clinical response.

- Administer TIBSOVO with or without food.
- Do not administer TIBSOVO with a high-fat meal [see Warnings and Precautions (5.2) and Clinical Pharmacology (12.3)].
- Do not split, crush, or chew TIBSOVO tablets.
- Administer TIBSOVO tablets orally about the same time each day.
- If a dose of TIBSOVO is vomited, do not administer a replacement dose; wait until the next scheduled dose is due.
- If a dose of TIBSOVO is missed or not taken at the usual time, administer the dose as soon as possible and at least 12 hours prior to the next scheduled dose. Return to the normal schedule the following day. Do not administer 2 doses within 12 hours.

Newly Diagnosed AML (Combination Regimen)

Start TIBSOVO administration on Cycle 1 Day 1 in combination with azacitidine 75 mg/m^2 subcutaneously or intravenously once daily on Days 1-7 (or Days 1-5 and 8-9) of each 28-day cycle [see Clinical Studies (14.1)]. Refer to the Prescribing Information for azacitidine for additional dosing information.

2.3 Monitoring and Dosage Modifications for Toxicities

Obtain an electrocardiogram (ECG) prior to treatment initiation. Monitor ECGs at least once weekly for the first 3 weeks of therapy and then at least once monthly for the duration of therapy [see Warnings and Precautions (5.2)]. Manage any abnormalities promptly.

Interrupt dosing or reduce dose for toxicities. See Table 1 for dosage modification guidelines.

Table 1: Recommended Dosage Modifications for TIBSOVO
Adverse Reactions | Recommended Action
- Differentiation syndrome [see Warnings and Precautions (5.1)] | - If differentiation syndrome is suspected, administer systemic corticosteroids and initiate hemodynamic monitoring until symptom resolution and for a minimum of 3 days. - Interrupt TIBSOVO if severe signs and/or symptoms persist for more than 48 hours after initiation of systemic corticosteroids. - Resume TIBSOVO when signs and symptoms improve to Grade 2 or lower.
- Noninfectious leukocytosis (white blood cell [WBC] count greater than 25 × 10^9/L or an absolute increase in total WBC of greater than 15 × 10^9/L from baseline) | - Initiate treatment with hydroxyurea, as per standard institutional practices, and leukapheresis if clinically indicated. - Taper hydroxyurea only after leukocytosis improves or resolves. - Interrupt TIBSOVO if leukocytosis is not improved with hydroxyurea, and then resume TIBSOVO at 500 mg daily when leukocytosis has resolved.
- QTc interval greater than 480 msec to 500 msec [see Warnings and Precautions (5.2) and Drug Interactions (7.1)] | - Monitor and supplement electrolyte levels as clinically indicated. - Review and adjust concomitant medications with known QTc interval-prolonging effects. - Interrupt TIBSOVO. - Restart TIBSOVO at 500 mg once daily after the QTc interval returns to less than or equal to 480 msec. - Monitor ECGs at least weekly for 2 weeks following resolution of QTc prolongation.
- QTc interval greater than 500 msec [see Warnings and Precautions (5.2) and Drug Interactions (7.1)] | - Monitor and supplement electrolyte levels as clinically indicated. - Review and adjust concomitant medications with known QTc interval-prolonging effects. - Interrupt TIBSOVO. - Resume TIBSOVO at a reduced dose of 250 mg once daily when QTc interval returns to within 30 msec of baseline or less than or equal to 480 msec. - Monitor ECGs at least weekly for 2 weeks following resolution of QTc prolongation. - Consider re-escalating the dose of TIBSOVO to 500 mg daily if an alternative etiology for QTc prolongation can be identified.
- QTc interval prolongation with signs/symptoms of life-threatening arrhythmia [see Warnings and Precautions (5.2)] | - Discontinue TIBSOVO permanently.
- Guillain-Barré syndrome [see Warnings and Precautions (5.3)] | - Discontinue TIBSOVO permanently.
- Other Grade 3 [Grade 1 is mild, Grade 2 is moderate, Grade 3 is severe, Grade 4 is life-threatening; grading based on Common Terminology Criteria for Adverse Events (CTCAE) version 4.03.] adverse reactions | As monotherapy in AML and MDS:; - Interrupt TIBSOVO until toxicity resolves to Grade 2 or lower. - Resume TIBSOVO at 250 mg once daily; may increase to 500 mg once daily if toxicities resolve to Grade 1 or lower. - If Grade 3 or higher toxicity recurs, discontinue TIBSOVO.; In cholangiocarcinoma, or in AML in combination with azacitidine:; - Interrupt TIBSOVO until toxicity resolves to Grade 1 or lower, or baseline, then resume at 500 mg daily (Grade 3 toxicity) or 250 mg daily (Grade 4 toxicity). - If Grade 3 toxicity recurs (a second time), reduce TIBSOVO dose to 250 mg daily until the toxicity resolves, then resume 500 mg daily. - If Grade 3 toxicity recurs (a third time), or Grade 4 toxicity recurs, discontinue TIBSOVO.

Patients with AML or MDS

Assess blood counts and blood chemistries prior to the initiation of TIBSOVO, at least once weekly for the first month, once every other week for the second month, and once monthly for the duration of therapy.

Monitor blood creatine phosphokinase weekly for the first month of therapy.

2.4 Dosage Modification for Use with Strong CYP3A4 Inhibitors

If a strong CYP3A4 inhibitor must be coadministered, reduce the TIBSOVO dose to 250 mg once daily. If the strong inhibitor is discontinued, increase the TIBSOVO dose (after at least 5 half-lives of the strong CYP3A4 inhibitor) to the recommended dose of 500 mg once daily.

3 DOSAGE FORMS AND STRENGTHS

Tablets: 250 mg as a blue oval-shaped film-coated tablet debossed "IVO" on one side and "250" on the other side.

4 CONTRAINDICATIONS

None.

5 WARNINGS AND PRECAUTIONS

5.1 Differentiation Syndrome in AML and MDS

Differentiation syndrome is associated with rapid proliferation and differentiation of myeloid cells and may be life-threatening or fatal.

Symptoms of differentiation syndrome in patients treated with TIBSOVO included noninfectious leukocytosis, peripheral edema, pyrexia, dyspnea, pleural effusion, hypotension, hypoxia, pulmonary edema, pneumonitis, pericardial effusion, rash, fluid overload, tumor lysis syndrome and creatinine increased.

In the combination study AG120-C-009, 15% (11/71) patients with newly diagnosed AML treated with TIBSOVO plus azacitidine experienced differentiation syndrome [see Adverse Reactions (6.1)]. Of the 11 patients with newly diagnosed AML who experienced differentiation syndrome with TIBSOVO plus azacitidine 8 (73%) recovered. Differentiation syndrome occurred as early as 3 days after start of therapy and during the first month on treatment.

In the monotherapy clinical trial AG120-C-001, 25% (7/28) of patients with newly diagnosed AML and 19% (34/179) of patients with relapsed or refractory AML treated with TIBSOVO experienced differentiation syndrome [see Adverse Reactions (6.1)]. Of the 7 patients with newly diagnosed AML who experienced differentiation syndrome, 6 (86%) patients recovered. Of the 34 patients with relapsed or refractory AML who experienced differentiation syndrome, 27 (79%) patients recovered after treatment or after dose interruption of TIBSOVO. Differentiation syndrome occurred as early as 1 day and up to 3 months after TIBSOVO initiation and has been observed with or without concomitant leukocytosis.

In the monotherapy clinical trial AG120-C-001, 11% (2/19) of patients with relapsed or refractory MDS treated with TIBSOVO experienced differentiation syndrome [see Adverse Reactions (6.1)]. Of the 2 patients who experienced differentiation syndrome, both recovered after treatment or after dose interruption of TIBSOVO. Differentiation syndrome occurred as early as 1 day and up to 3 months after TIBSOVO initiation and has been observed with or without concomitant leukocytosis.

If differentiation syndrome is suspected, initiate dexamethasone 10 mg IV every 12 hours (or an equivalent dose of an alternative oral or IV corticosteroid) and hemodynamic monitoring until improvement [see Dosage and Administration (2.3)]. If concomitant noninfectious leukocytosis is observed, initiate treatment with hydroxyurea or leukapheresis, as clinically indicated. Taper corticosteroids and hydroxyurea after resolution of symptoms and administer corticosteroids for a minimum of 3 days. Symptoms of differentiation syndrome may recur with premature discontinuation of corticosteroid and/or hydroxyurea treatment. If severe signs and/or symptoms persist for more than 48 hours after initiation of corticosteroids, interrupt TIBSOVO until signs and symptoms are no longer severe [see Dosage and Administration (2.3)].

5.2 QTc Interval Prolongation

Patients treated with TIBSOVO can develop QT (QTc) prolongation and ventricular arrhythmias [see Clinical Pharmacology (12.2)].

Of the 71 patients with newly diagnosed AML treated with TIBSOVO in combination with azacitidine in the clinical trial (Study AG120-C-009), 10 (14%) were found to have a heart-rate corrected QT interval (using Fridericia's method) (QTcF) greater than 500 msec and 15 out of 69 (22%) had an increase from baseline QTcF greater than 60 msec [see Adverse Reactions (6.1)]. The clinical trial excluded patients with a QTcF ≥ 470 msec or other factors that increased the risk of QT prolongation or arrhythmic events (e.g. NYHA Class III or IV congestive heart failure, hypokalemia, family history of long QT interval syndrome).

Of the 265 patients with hematological malignancies, including patients with AML and MDS, treated with TIBSOVO monotherapy in the clinical trial (AG120-C-001), 9% were found to have a QTc interval greater than 500 msec and 14% of patients had an increase from baseline QTc greater than 60 msec [see Adverse Reactions (6.1)]. One patient developed ventricular fibrillation attributed to TIBSOVO. The clinical trial excluded patients with baseline QTc of ≥ 450 msec (unless the QTc ≥ 450 msec was due to a pre-existing bundle branch block) or with a history of long QT syndrome or uncontrolled or significant cardiovascular disease.

Of the 123 patients with cholangiocarcinoma treated with TIBSOVO in the clinical trial (Study AG120-C-005), 2% were found to have a QTc interval greater than 500 msec and 5% of patients had an increase from baseline QTc greater than 60 msec [see Adverse Reactions (6.1)]. The clinical trial excluded patients with a heart-rate corrected QT interval (using Fridericia's formula) (QTcF) ≥ 450 msec or other factors that increased the risk of QT prolongation or arrhythmic events (e.g., heart failure, hypokalemia, family history of long QT interval syndrome).

Concomitant use of TIBSOVO with drugs known to prolong the QTc interval (e.g., anti-arrhythmic medicines, fluoroquinolones, triazole anti-fungals, 5-HT3 receptor antagonists) and CYP3A4 inhibitors may increase the risk of QTc interval prolongation [see Drug Interactions (7.1), Clinical Pharmacology (12.2)]. Conduct monitoring of electrocardiograms (ECGs) and electrolytes [see Dosage and Administration (2.3)].

In patients with congenital long QTc syndrome, congestive heart failure, electrolyte abnormalities, or those who are taking medications known to prolong the QTc interval, more frequent monitoring may be necessary.

Interrupt TIBSOVO if QTc increases to greater than 480 msec and less than 500 msec. Interrupt and reduce TIBSOVO if QTc increases to greater than 500 msec. Permanently discontinue TIBSOVO in patients who develop QTc interval prolongation with signs or symptoms of life-threatening arrhythmia [See Dosage and Administration (2.3)].

5.3 Guillain-Barré Syndrome

Guillain-Barré syndrome can develop in patients treated with TIBSOVO. Guillain-Barré syndrome occurred in 0.8% (2/265) of patients treated with TIBSOVO in study AG120-C-001 [see Adverse Reactions (6.1)].

Monitor patients taking TIBSOVO for onset of new signs or symptoms of motor and/or sensory neuropathy such as unilateral or bilateral weakness, sensory alterations, paresthesias, or difficulty breathing. Permanently discontinue TIBSOVO in patients who are diagnosed with Guillain-Barré syndrome [see Dosage and Administration (2.3)].

6 ADVERSE REACTIONS

The following clinically significant adverse reactions are described elsewhere in the labeling:

- Differentiation Syndrome in AML and MDS [see Warnings and Precautions (5.1)]
- QTc Interval Prolongation [see Warnings and Precautions (5.2)]
- Guillain-Barré Syndrome [see Warnings and Precautions (5.3)]

6.1 Clinical Trials Experience

Because clinical trials are conducted under widely varying conditions, adverse reaction rates observed in the clinical trials of a drug cannot be directly compared to rates in the clinical trials of another drug and may not reflect the rates observed in practice.

Acute Myeloid Leukemia

In AML, the safety population reflects exposure to TIBSOVO at 500 mg daily in combination with azacitidine or as monotherapy in patients in Studies AG120-C-009 (N=71) and AG120-C-001 (N=213), respectively [see Clinical Studies (14.1 and 14.2)]. In this safety population, the most common adverse reactions including laboratory abnormalities (≥ 25% in either trial) were leukocytes decreased, diarrhea, hemoglobin decreased, platelets decreased, glucose increased, fatigue, alkaline phosphatase increased, edema, potassium decreased, nausea, vomiting, phosphatase decreased, decreased appetite, sodium decreased, leukocytosis, magnesium decreased, aspartate aminotransferase increased, arthralgia, dyspnea, uric acid increased, abdominal pain, creatinine increased, mucositis, rash, electrocardiogram QT prolonged, differentiation syndrome, calcium decreased, neutrophils decreased, and myalgia.

Newly Diagnosed AML

TIBSOVO in Combination with Azacitidine

The safety of TIBSOVO was evaluated in AML patients treated in combination with azacitidine, in Study AG120-C-009 [see Clinical Studies (14.1)]. Patients received at least one dose of either TIBSOVO 500 mg daily (N=71) or placebo (N=73). Among patients who received TIBSOVO in combination with azacitidine, the median duration of exposure to TIBSOVO was 6 months (range 0 to 33 months). Thirty-four patients (48%) were exposed to TIBSOVO for at least 6 months and 22 patients (31%) were exposed for at least 1 year.

Common (≥ 5%) serious adverse reactions in patients who received TIBSOVO in combination with azacitidine included differentiation syndrome (8%).

Fatal adverse reactions occurred in 4% of patients who received TIBSOVO in combination with azacitidine, due to differentiation syndrome (3%) and one case of cerebral ischemia.

Adverse reactions leading to discontinuation of TIBSOVO in ≥2% of patients were differentiation syndrome (3%) and pulmonary embolism (3%).

The most common (>5%) adverse reactions leading to dose interruption of TIBSOVO were neutropenia (25%), electrocardiogram QT prolonged (7%), and thrombocytopenia (7%).

Adverse reactions leading to dose reduction of TIBSOVO included electrocardiogram QT prolonged (8%), neutropenia (8%), and thrombocytopenia (1%).

The most common adverse reactions and laboratory abnormalities observed in Study AG120-C-009 are shown in Tables 2 and 3.

Table 2: Adverse Reactions (≥10%) in Patients with AML Who Received TIBSOVO + azacitidine with a Difference Between Arms of ≥ 2% Compared with Placebo + azacitidine in AG120-C-009
 | TIBSOVO + Azacitidine N=71 |  | Placebo + Azacitidine N=73
Body System Adverse Reaction | All Grades n (%) | Grade ≥3 n (%) | All Grades n (%) | Grade ≥3 n (%)
Gastrointestinal disorders
Nausea | 30 (42) | 2 (3) | 28 (38) | 3 (4)
Vomiting [Grouped term includes vomiting and retching.] | 29 (41) | 0 | 20 (27) | 1 (1)
Investigations
Electrocardiogram QT prolonged | 14 (20) | 7 (10) | 5 (7) | 2 (3)
Psychiatric Disorders
Insomnia | 13 (18) | 1 (1) | 9 (12) | 0
Blood system and lymphatic system disorders
Differentiation Syndrome [Differentiation syndrome can be associated with other commonly reported events such as peripheral edema, leukocytosis, pyrexia, dyspnea, pleural effusion, hypotension, hypoxia, pulmonary edema, pneumonia, pericardial effusion, rash, fluid overload, tumor lysis syndrome, and creatinine increased.] | 11 (15) | 7 (10) | 6 (8) | 6 (8)
Leukocytosis [Grouped term includes leukocytosis, white blood cell count increased.] | 9 (13) | 0 | 1 (1) | 0
Vascular disorders
Hematoma [Grouped term includes hematoma, eye hematoma, catheter site hematoma, oral mucosa hematoma, spontaneous hematoma, application site hematoma, injection site hematoma, periorbital hematoma.] | 11 (15) | 0 | 3 (4) | 0
Hypertension [Grouped term includes blood pressure increased, essential hypertension, and hypertension.] | 9 (13) | 3 (4) | 6 (8) | 4 (5)
Musculoskeletal and connective tissue disorders
Arthralgia [Grouped term includes pain in extremity, arthralgia, back pain, musculoskeletal stiffness, cancer pain, and neck pain.] | 21 (30) | 3 (4) | 6 (8) | 1 (1)
Respiratory, thoracic and mediastinal disorders
Dyspnea [Grouped term includes dyspnea, dyspnea exertional, hypoxia, respiration failure.] | 14 (20) | 2 (3) | 11 (15) | 4 (5)
Nervous system disorders
Headache | 8 (11) | 0 | 2 (3) | 0

Table 3: Select Laboratory Abnormalities [Laboratory abnormality is defined as new or worsened by at least one grade from baseline, or if baseline is unknown.] , [The denominator used to calculate percentages is the number of treated subjects who can be evaluated for CTCAE criteria for each parameter in each arm.] (≥10%) That Worsened from Baseline in Patients with AML Who Received TIBSOVO + azacitidine in AG120-C-009
 | TIBSOVO + Azacitidine N=71 |  | Placebo + Azacitidine N=73
Parameter | All Grades n (%) | Grade ≥ 3 n (%) | All Grades n (%) | Grade ≥ 3 n (%)
Hematology Parameters
Leukocytes decreased | 46 (65) | 39 (55) | 47 (64) | 42 (58)
Platelets decreased | 41 (58) | 30 (42) | 52 (71) | 42 (58)
Hemoglobin decreased | 40 (56) | 33 (46) | 48 (66) | 42 (58)
Neutrophils decreased | 18 (25) | 16 (23) | 25 (35) | 23 (32)
Lymphocytes increased | 17 (24) | 1 (1) | 7 (10) | 1 (1)
Chemistry Parameters
Glucose increased | 40 (56) | 9 (13) | 34 (47) | 8 (11)
Phosphate decreased | 29 (41) | 7 (10) | 25 (34) | 9 (12)
Aspartate Aminotransferase increased | 26 (37) | 0 | 17 (23) | 0
Magnesium decreased | 25 (35) | 0 | 19 (26) | 0
Alkaline Phosphatase increased | 23 (32) | 0 | 21 (29) | 0
Potassium increased | 17 (24) | 2 (3) | 9 (12) | 1 (1)

TIBSOVO Monotherapy

The safety profile of single-agent TIBSOVO was studied in 28 adults with newly diagnosed AML treated with 500 mg daily [see Clinical Studies (14.1)]. The median duration of exposure to TIBSOVO was 4.3 months (range 0.3 to 40.9 months). Ten patients (36%) were exposed to TIBSOVO for at least 6 months and 6 patients (21%) were exposed for at least 1 year.

Common (≥ 5%) serious adverse reactions included differentiation syndrome (18%), electrocardiogram QT prolonged (7%), and fatigue (7%). There was one case of posterior reversible encephalopathy syndrome (PRES).

Common (≥ 10%) adverse reactions leading to dose interruption included electrocardiogram QT prolonged (14%) and differentiation syndrome (11%). Two (7%) patients required a dose reduction due to electrocardiogram QT prolonged. One patient each required permanent discontinuation due to diarrhea and PRES.

The most common adverse reactions reported in the trial are shown in Table 4.

Table 4: Adverse Reactions Reported in ≥ 10% (Any Grade) or ≥ 5% (Grade ≥ 3) of Patients with Newly Diagnosed AML in AG120-C-001
 | TIBSOVO (500 mg daily) N=28
Body System Adverse Reaction | All Grades n (%) | Grade ≥ 3 n (%)
Gastrointestinal disorders
Diarrhea | 17 (61) | 2 (7)
Nausea | 10 (36) | 2 (7)
Abdominal pain [Grouped term includes abdominal pain, upper abdominal pain, abdominal discomfort, and abdominal tenderness.] | 8 (29) | 1 (4)
Constipation | 6 (21) | 1 (4)
Vomiting | 6 (21) | 1 (4)
Mucositis [Grouped term includes aphthous ulcer, esophageal pain, esophagitis, gingival pain, gingivitis, mouth ulceration, mucosal inflammation, oral pain, oropharyngeal pain, proctalgia, and stomatitis.] | 6 (21) | 0
Dyspepsia | 3 (11) | 0
General disorders and administration site conditions
Fatigue [Grouped term includes asthenia and fatigue.] | 14 (50) | 4 (14)
Edema [Grouped term includes edema, face edema, fluid overload, fluid retention, hypervolemia, peripheral edema, and swelling face.] | 12 (43) | 0
Metabolism and nutrition disorders
Decreased appetite | 11 (39) | 1 (4)
Blood system and lymphatic system disorders
Leukocytosis [Grouped term includes leukocytosis, hyperleukocytosis, and increased white blood cell count.] | 10 (36) | 2 (7)
Differentiation Syndrome [Differentiation syndrome can be associated with other commonly reported events such as peripheral edema, leukocytosis, pyrexia, dyspnea, pleural effusion, hypotension, hypoxia, pulmonary edema, pneumonia, pericardial effusion, rash, fluid overload, tumor lysis syndrome, and creatinine increased.] | 7 (25) | 3 (11)
Musculoskeletal and connective tissue disorders
Arthralgia [Grouped term includes arthralgia, back pain, musculoskeletal stiffness, neck pain, and pain in extremity.] | 9 (32) | 1 (4)
Myalgia [Grouped term includes myalgia, muscular weakness, musculoskeletal pain, musculoskeletal chest pain, musculoskeletal discomfort, and myalgia intercostal.] | 7 (25) | 1 (4)
Respiratory, thoracic, and mediastinal disorders
Dyspnea [Grouped term includes dyspnea, dyspnea exertional, hypoxia, and respiratory failure.] | 8 (29) | 1 (4)
Cough [Grouped term includes cough, productive cough, and upper airway cough syndrome.] | 4 (14) | 0
Investigations
Electrocardiogram QT prolonged | 6 (21) | 3 (11)
Weight decreased | 3 (11) | 0
Nervous system disorders
Dizziness | 6 (21) | 0
Neuropathy [Grouped term includes burning sensation, lumbosacral plexopathy, neuropathy peripheral, paresthesia, and peripheral motor neuropathy.] | 4 (14) | 0
Headache | 3 (11) | 0
Skin and subcutaneous tissue disorders
Pruritus | 4 (14) | 1 (4)
Rash [Grouped term includes dermatitis acneiform, dermatitis, rash, rash maculo-papular, urticaria, rash erythematous, rash macular, rash pruritic, rash generalized, rash papular, skin exfoliation, and skin ulcer.] | 4 (14) | 1 (4)

Changes in selected post-baseline laboratory values that were observed in patients with newly diagnosed AML are shown in Table 5.

Table 5: Most Common (≥ 10%) or ≥ 5% (Grade ≥ 3) New or Worsening Laboratory Abnormalities Reported in Patients with Newly Diagnosed AML [Laboratory abnormality is defined as new or worsened by at least one grade from baseline, or if baseline is unknown.] in AG120-C-001
 | TIBSOVO (500 mg daily) N=28
Parameter | All Grades n (%) | Grade ≥ 3 n (%)
Hemoglobin decreased | 15 (54) | 12 (43)
Alkaline phosphatase increased | 13 (46) | 0
Potassium decreased | 12 (43) | 3 (11)
Sodium decreased | 11 (39) | 1 (4)
Uric acid increased | 8 (29) | 1 (4)
Aspartate aminotransferase increased | 8 (29) | 1 (4)
Creatinine increased | 8 (29) | 0
Magnesium decreased | 7 (25) | 0
Calcium decreased | 7 (25) | 1 (4)
Phosphate decreased | 6 (21) | 2 (7)
Alanine aminotransferase increased | 4 (14) | 1 (4)

Relapsed or Refractory AML

The safety profile of single-agent TIBSOVO was studied in 179 adults with relapsed or refractory AML treated with 500 mg daily [see Clinical Studies (14.2)].

The median duration of exposure to TIBSOVO was 3.9 months (range 0.1 to 39.5 months). Sixty-five patients (36%) were exposed to TIBSOVO for at least 6 months and 16 patients (9%) were exposed for at least 1 year.

Serious adverse reactions (≥ 5%) were differentiation syndrome (10%), leukocytosis (10%), and electrocardiogram QT prolonged (7%). There was one case of progressive multifocal leukoencephalopathy (PML).

The most common adverse reactions leading to dose interruption were electrocardiogram QT prolonged (7%), differentiation syndrome (3%), leukocytosis (3%) and dyspnea (3%). Five out of 179 patients (3%) required a dose reduction due to an adverse reaction.

Adverse reactions leading to a dose reduction included electrocardiogram QT prolonged (1%), diarrhea (1%), nausea (1%), decreased hemoglobin (1%), and increased transaminases (1%).

Adverse reactions leading to permanent discontinuation included Guillain-Barré syndrome (1%), rash (1%), stomatitis (1%), and creatinine increased (1%).

The most common adverse reactions reported in the trial are shown in Table 6.

Table 6: Adverse Reactions Reported in ≥ 10% (Any Grade) or ≥ 5% (Grade ≥ 3) of Patients with Relapsed or Refractory AML
 | TIBSOVO (500 mg daily) N=179
Body System Adverse Reaction | All Grades n (%) | Grade ≥ 3 n (%)
General disorders and administration site conditions
Fatigue [Grouped term includes asthenia and fatigue.] | 69 (39) | 6 (3)
Edema [Grouped term includes peripheral edema, edema, fluid overload, fluid retention, and face edema.] | 57 (32) | 2 (1)
Pyrexia | 41 (23) | 2 (1)
Chest pain [Grouped term includes angina pectoris, chest pain, chest discomfort, and non-cardiac chest pain] | 29 (16) | 5 (3)
Blood system and lymphatic system disorders
Leukocytosis [Grouped term includes leukocytosis, hyperleukocytosis, and increased white blood cell count.] | 68 (38) | 15 (8)
Differentiation Syndrome [Differentiation syndrome can be associated with other commonly reported events such as peripheral edema, leukocytosis, pyrexia, dyspnea, pleural effusion, hypotension, hypoxia, pulmonary edema, pneumonia, pericardial effusion, rash, fluid overload, tumor lysis syndrome, and creatinine increased.] | 34 (19) | 23 (13)
Musculoskeletal and connective tissue disorders
Arthralgia [Grouped term includes arthralgia, back pain, musculoskeletal stiffness, neck pain, and pain in extremity.] | 64 (36) | 8 (4)
Myalgia [Grouped term includes myalgia, muscular weakness, musculoskeletal pain, musculoskeletal chest pain, musculoskeletal discomfort, and myalgia intercostal.] | 33 (18) | 1 (1)
Gastrointestinal disorders
Diarrhea | 60 (34) | 4 (2)
Nausea | 56 (31) | 1 (1)
Mucositis [Grouped term includes aphthous ulcer, esophageal pain, esophagitis, gingival pain, gingivitis, mouth ulceration, mucosal inflammation, oral pain, oropharyngeal pain, proctalgia, and stomatitis.] | 51 (28) | 6 (3)
Constipation | 35 (20) | 1 (1)
Vomiting [Grouped term includes vomiting and retching.] | 32 (18) | 2 (1)
Abdominal pain [Grouped term includes abdominal pain, upper abdominal pain, abdominal discomfort, and abdominal tenderness.] | 29 (16) | 2 (1)
Respiratory, thoracic, and mediastinal disorders
Dyspnea [Grouped term includes dyspnea, respiratory failure, hypoxia, and dyspnea exertional.] | 59 (33) | 16 (9)
Cough [Grouped term includes cough, productive cough, and upper airway cough syndrome.] | 40 (22) | 1 (<1)
Pleural effusion | 23 (13) | 5 (3)
Investigations
Electrocardiogram QT prolonged | 46 (26) | 18 (10)
Skin and subcutaneous tissue disorders
Rash [Grouped term includes dermatitis acneiform, dermatitis, rash, rash maculo-papular, urticaria, rash erythematous, rash macular, rash pruritic, rash generalized, rash papular, skin exfoliation, and skin ulcer.] | 46 (26) | 4 (2)
Metabolism and nutrition disorders
Decreased appetite | 33 (18) | 3 (2)
Tumor lysis syndrome | 14 (8) | 11 (6)
Nervous system disorders
Headache | 28 (16) | 0
Neuropathy [Grouped term includes ataxia, burning sensation, gait disturbance, Guillain-Barré syndrome, neuropathy peripheral, paresthesia, peripheral sensory neuropathy, peripheral motor neuropathy, and sensory disturbance.] | 21 (12) | 2 (1)
Vascular disorders
Hypotension [Grouped term includes hypotension and orthostatic hypotension.] | 22 (12) | 7 (4)

Changes in selected post-baseline laboratory values that were observed in patients with relapsed or refractory AML are shown in Table 7.

Table 7: Most Common (≥ 10%) or ≥ 5% (Grade ≥ 3) New or Worsening Laboratory Abnormalities Reported in Patients with Relapsed or Refractory AML [Laboratory abnormality is defined as new or worsened by at least one grade from baseline, or if baseline is unknown.]
 | TIBSOVO (500 mg daily) N=179
Parameter | All Grades n (%) | Grade ≥ 3 n (%)
Hemoglobin decreased | 108 (60) | 83 (46)
Sodium decreased | 69 (39) | 8 (4)
Magnesium decreased | 68 (38) | 0
Uric acid increased | 57 (32) | 11 (6)
Potassium decreased | 55 (31) | 11 (6)
Alkaline phosphatase increased | 49 (27) | 1 (1)
Aspartate aminotransferase increased | 49 (27) | 1 (1)
Phosphate decreased | 45 (25) | 15 (8)
Creatinine increased | 42 (23) | 2 (1)
Alanine aminotransferase increased | 26 (15) | 2 (1)
Bilirubin increased | 28 (16) | 1 (1)

Relapsed or Refractory Myelodysplastic Syndromes

The safety of TIBSOVO was evaluated in 19 adults with relapsed or refractory MDS treated with 500 mg daily in AG120-C-001 [see Clinical Studies (14.3)]. The median duration of exposure to TIBSOVO was 9.3 months (range 3.3 to 78.8 months). Fourteen patients (74%) were exposed to TIBSOVO for at least 6 months and 8 patients (42%) were exposed for at least 1 year.

Serious adverse reactions in ≥ 5% included differentiation syndrome (11%), fatigue (5%), and rash (5%).

Permanent discontinuation of TIBSOVO due to an adverse reaction occurred in 5% of patients. The adverse reaction which resulted in permanent discontinuation of TIBSOVO was fatigue.

Adverse reactions leading to dosage interruption of TIBSOVO occurred in 16% of patients. Adverse reactions which required dosage interruption in ≥ 5% were differentiation syndrome, leukocytosis, and rash.

Dose reductions of TIBSOVO due to an adverse reaction occurred in 16% of patients. Adverse reactions which required a dose reduction in ≥ 5% included differentiation syndrome, fatigue, and rash.

The most common (≥ 25%) adverse reactions, including laboratory abnormalities, were creatinine increased, hemoglobin decrease, arthralgia, albumin decreased, aspartate aminotransferase increased, fatigue, diarrhea, cough, sodium decreased, mucositis, decreased appetite, myalgia, phosphate decreased, pruritus, and rash.

Table 8 summarizes the adverse reactions in AG120-C-001.

Table 8: Adverse Reactions ≥ 10% in Patients with Relapsed or Refractory MDS in AG120-C-001
 | TIBSOVO (500 mg daily) N=19
Body System Adverse Reaction | All Grades % | Grade 3 or 4 %
Musculoskeletal and connective tissue disorders
Arthralgia [Grouped term includes arthralgia, back pain, pain in extremity, flank pain, joint swelling, and neck pain.] | 42 | 16
Myalgia [Grouped term includes myalgia, muscle spasms, muscle discomfort, and musculoskeletal chest pain.] | 26 | 0
General disorders and administration site conditions
Fatigue [Grouped term includes fatigue and asthenia.] | 37 | 11
Respiratory, thoracic, and mediastinal disorders
Cough | 32 | 0
Dyspnea [Grouped term includes dyspnea and dyspnea exertional.] | 21 | 0
Gastrointestinal disorders
Diarrhea | 32 | 0
Mucositis [Grouped term includes oropharyngeal pain, gingivitis, mouth ulceration, stomatitis.] | 26 | 5
Constipation | 16 | 0
Nausea | 16 | 0
Skin and subcutaneous tissue disorders
Pruritus | 26 | 0
Rash [Grouped term includes rash, catheter site erythema, and urticaria.] | 26 | 0
Metabolism and nutrition disorders
Decreased appetite | 26 | 0
Blood system and lymphatic system disorders
Leukocytosis [Grouped term includes leukocytosis, hyperleukocytosis, and white blood cell count increased.] | 16 | 5
Differentiation Syndrome | 11 | 0
Nervous system disorders
Headache | 16 | 0
Vascular disorders
Hypertension | 16 | 16
Investigations
Electrocardiogram QT prolonged | 11 | 0

Table 9 summarizes laboratory abnormalities in AG120-C-001.

Table 9: Select Laboratory Abnormalities (≥ 15%) That Worsened from Baseline in Patients with Relapsed or Refractory MDS in AG120-C-001
 | TIBSOVO [Laboratory abnormality is defined as new or worsened by at least one grade from baseline, or if baseline is unknown.] N=19
Laboratory Abnormality | All Grades % | Grade 3 or 4 %
Creatinine increased | 95 | 5
Hemoglobin decreased | 42 | 32
Albumin decreased | 37 | 0
Aspartate Aminotransferase increased | 37 | 5
Sodium decreased | 32 | 5
Phosphate decreased | 26 | 5
Alanine Aminotransferase increased | 21 | 5
Bilirubin increased | 21 | 0
Magnesium decreased | 21 | 0
Alkaline Phosphatase increased | 16 | 0
Potassium increased | 16 | 0

Locally Advanced or Metastatic Cholangiocarcinoma

The safety of TIBSOVO was studied in patients with previously treated, locally advanced or metastatic cholangiocarcinoma in Study AG120-C-005 [see Clinical Studies (14.4)]. Patients received at least one dose of either TIBSOVO 500 mg daily (N=123) or placebo (N=59). The median duration of treatment was 2.8 months (range 0.1 to 34.4 months) with TIBSOVO.

Serious adverse reactions occurred in 34% of patients receiving TIBSOVO. Serious adverse reactions in ≥2% of patients in the TIBSOVO arm were pneumonia, ascites, hyperbilirubinemia, and jaundice cholestatic.

Fatal adverse reactions occurred in 4.9% of patients receiving TIBSOVO, including sepsis (1.6%) and pneumonia, intestinal obstruction, pulmonary embolism, and hepatic encephalopathy (each 0.8%).

TIBSOVO was permanently discontinued in 7% of patients. The most common adverse reactions leading to permanent discontinuation was acute kidney injury (1.6%).

Dose interruptions due to adverse reactions occurred in 29% of patients treated with TIBSOVO. The most common (>2%) adverse reactions leading to dose interruption were hyperbilirubinemia, alanine aminotransferase increased, aspartate aminotransferase increased, ascites, and fatigue.

Dose reductions of TIBSOVO due to an adverse reaction occurred in 4.1% of patients. Adverse reactions leading to dose reduction were electrocardiogram QT prolonged (3.3%) and neuropathy peripheral (0.8%).

The most common adverse reactions (≥15%) were fatigue, nausea, abdominal pain, diarrhea, cough, decreased appetite, ascites, vomiting, anemia, and rash.

Adverse reactions and laboratory abnormalities observed in Study AG120-C-005 are shown in Tables 10 and 11.

Table 10: Adverse Reactions Occurring in ≥ 10% of Patients Receiving TIBSOVO in Study AG120-C-005
 | TIBSOVO (500 mg daily) N=123 |  | Placebo N=59
Body System Adverse Reaction | All Grades n (%) | Grade ≥ 3 n (%) | All Grades n (%) | Grade ≥ 3 n (%)
General disorders and administration site conditions
Fatigue [Grouped term includes asthenia and fatigue.] | 53 (43) | 4 (3) | 18 (31) | 3 (5)
Gastrointestinal disorders
Nausea | 51 (41) | 3 (2) | 17 (29) | 1 (2)
Diarrhea | 43 (35) | 0 | 10 (17) | 0
Abdominal pain [Grouped term includes abdominal pain, abdominal pain upper, abdominal discomfort, abdominal pain lower, epigastric discomfort, abdominal tenderness, and gastrointestinal pain.] | 43 (35) | 3 (2) | 13 (22) | 2 (3)
Ascites | 28 (23) | 11 (9) | 9 (15) | 4 (7)
Vomiting [Grouped term includes vomiting and retching.] | 28 (23) | 3 (2) | 12 (20) | 0
Respiratory, thoracic, and mediastinal disorders
Cough [Grouped term includes cough and productive cough.] | 33 (27) | 0 | 5 (9) | 0
Metabolism and nutrition disorders
Decreased appetite | 30 (24) | 2 (2) | 11 (19) | 0
Blood and lymphatic system disorders
Anemia | 22 (18) | 8 (7) | 3 (5) | 0
Skin and subcutaneous tissue disorders
Rash [Grouped term includes rash, rash maculo-papular, erythema, rash macular, dermatitis exfoliative generalized, drug eruption, and drug hypersensitivity.] | 19 (15) | 1 (1) | 4 (7) | 0
Nervous system disorders
Headache | 16 (13) | 0 | 4 (7) | 0
Neuropathy peripheral [Grouped term includes neuropathy peripheral, peripheral sensory neuropathy, and paresthesia.] | 13 (11) | 0 | 0 | 0
Investigations
Electrocardiogram QT prolonged | 12 (10) | 2 (2) | 2 (3) | 0

Table 11: Selected Laboratory Abnormalities Occurring in ≥ 10% of Patients Receiving TIBSOVO in Study AG120-C-005 [Laboratory abnormality is defined as new or worsened by at least one grade from baseline, or baseline is unknown.]
 | TIBSOVO (500 mg daily) N=123 |  | Placebo N=59
Parameter | All Grades n (%) | Grade ≥ 3 n (%) | All Grades n (%) | Grade ≥ 3 n (%)
AST increased | 41 (34) | 5 (4) | 14 (24) | 1 (2)
Bilirubin increased | 36 (30) | 15 (13) | 11 (19) | 2 (3)
Hemoglobin decreased | 48 (40) | 8 (7) | 14 (25) | 0

7 DRUG INTERACTIONS

7.1 Effect of Other Drugs on Ivosidenib

Strong or Moderate CYP3A4 Inhibitors
Clinical Impact | - Co-administration of TIBSOVO with strong or moderate CYP3A4 inhibitors increased ivosidenib plasma concentrations [see Clinical Pharmacology (12.3)]. - Increased ivosidenib plasma concentrations may increase the risk of QTc interval prolongation [see Warnings and Precautions (5.2)].
Prevention or Management | - Consider alternative therapies that are not strong or moderate CYP3A4 inhibitors during treatment with TIBSOVO. - If co-administration of a strong CYP3A4 inhibitor is unavoidable, reduce TIBSOVO to 250 mg once daily [see Dosage and Administration (2.3)]. - Monitor patients for increased risk of QTc interval prolongation [see Warnings and Precautions (5.2)].
Strong CYP3A4 Inducers
Clinical Impact | - Co-administration of TIBSOVO with strong CYP3A4 inducers decreased ivosidenib plasma concentrations [see Clinical Pharmacology (12.3)].
Prevention or Management | - Avoid co-administration of strong CYP3A4 inducers with TIBSOVO.
QTc Prolonging Drugs
Clinical Impact | - Co-administration of TIBSOVO with QTc prolonging drugs may increase the risk of QTc interval prolongation [see Warnings and Precautions (5.2)].
Prevention or Management | - Avoid co-administration of QTc prolonging drugs with TIBSOVO or replace with alternative therapies. - If co-administration of a QTc prolonging drug is unavoidable, monitor patients for increased risk of QTc interval prolongation [see Warnings and Precautions (5.2)].

7.2 Effect of Ivosidenib on Other Drugs

Ivosidenib induces CYP3A4 and may induce CYP2C9. Co-administration will decrease concentrations of drugs that are sensitive CYP3A4 substrates and may decrease concentrations of drugs that are sensitive CYP2C9 substrates [see Clinical Pharmacology (12.3)]. Use alternative therapies that are not sensitive substrates of CYP3A4 and CYP2C9 during TIBSOVO treatment. If co-administration of TIBSOVO with sensitive CYP3A4 substrates or CYP2C9 substrates is unavoidable, monitor patients for loss of therapeutic effect of these drugs.

Do not administer TIBSOVO with anti-fungal agents that are substrates of CYP3A4 due to expected loss of antifungal efficacy.

Co-administration of TIBSOVO may decrease the concentrations of hormonal contraceptives, consider alternative methods of contraception in patients receiving TIBSOVO.

8 USE IN SPECIFIC POPULATIONS

8.1 Pregnancy

Risk Summary

Based on animal embryo-fetal toxicity studies, TIBSOVO may cause fetal harm when administered to a pregnant woman. There are no available data on TIBSOVO use in pregnant women to inform a drug-associated risk of major birth defects and miscarriage. In animal embryo-fetal toxicity studies, oral administration of ivosidenib to pregnant rats and rabbits during organogenesis was associated with embryo-fetal mortality and alterations to growth starting at 2 times the steady state clinical exposure based on the AUC at the recommended human dose (see Data). If this drug is used during pregnancy, or if the patient becomes pregnant while taking this drug, advise the patient of the potential risk to a fetus.

The background risk of major birth defects and miscarriage for the indicated population is unknown. Adverse outcomes in pregnancy occur regardless of the health of the mother or the use of medications. In the U.S. general population, the estimated background risk of major birth defects and miscarriage in clinically recognized pregnancies is 2%-4% and 15%-20%, respectively.

Data

Animal Data

Ivosidenib administered to pregnant rats at a dose of 500 mg/kg/day during organogenesis (gestation days 6-17) was associated with adverse embryo-fetal effects including lower fetal weights, and skeletal variations. These effects occurred in rats at approximately 2 times the human exposure at the recommended dose of 500 mg daily.

In pregnant rabbits treated during organogenesis (gestation days 7-20), ivosidenib was maternally toxic at doses of 180 mg/kg/day (exposure approximately 3.9 times the human exposure at the recommended dose of 500 mg daily) and caused spontaneous abortions as well as decreased fetal weights, skeletal variations, and visceral variations.

8.2 Lactation

Risk Summary

There are no data on the presence of ivosidenib or its metabolites in human milk, the effects on the breastfed child, or the effects on milk production. Because many drugs are excreted in human milk and because of the potential for adverse reactions in breastfed children, advise women not to breastfeed during treatment with TIBSOVO and for 1 month after the last dose.

8.4 Pediatric Use

The safety and effectiveness of TIBSOVO in pediatric patients have not been established.

8.5 Geriatric Use

Of the 304 patients who received TIBSOVO in the clinical studies for AML and MDS, 75% were 65 years of age or older and 35% were 75 years or older.

Of the 124 patients with cholangiocarcinoma treated with TIBSOVO in Study AG120-C-005, 37% were 65 years of age or older and 11% were 75 years or older.

No overall differences in effectiveness or safety were observed between patients who were 65 years and older compared to younger patients.

8.6 Renal Impairment

No modification of the starting dose is recommended for patients with mild or moderate renal impairment (eGFR ≥ 30 mL/min/1.73m^2, MDRD). The pharmacokinetics and safety of ivosidenib in patients with severe renal impairment (eGFR < 30 mL/min/1.73m^2, MDRD) or renal impairment requiring dialysis are unknown [see Clinical Pharmacology (12.3)]. For patients with pre-existing severe renal impairment or who are requiring dialysis, consider the risks and potential benefits before initiating treatment with TIBSOVO.

8.7 Hepatic Impairment

No modification of the starting dose is recommended for patients with mild or moderate (Child-Pugh A or B) hepatic impairment [see Clinical Pharmacology (12.3)]. The pharmacokinetics and safety of ivosidenib in patients with severe hepatic impairment (Child-Pugh C) are unknown. For patients with pre-existing severe hepatic impairment, consider the risks and potential benefits before initiating treatment with TIBSOVO.

11 DESCRIPTION

TIBSOVO (ivosidenib) is an inhibitor of isocitrate dehydrogenase 1 (IDH1) enzyme. The chemical name is (2S)-N-{(1S)-1-(2-chlorophenyl)-2-[(3,3-difluorocyclobutyl)-amino]-2-oxoethyl}-1-(4-cyanopyridin-2-yl)-N-(5-fluoropyridin-3-yl)-5-oxopyrrolidine-2-carboxamide. The chemical structure is:

The molecular formula is C28H22ClF3N6O3 and the molecular weight is 583.0 g/mol. Ivosidenib is practically insoluble in aqueous solutions between pH 1.2 and 7.4.

TIBSOVO (ivosidenib) is available as a film-coated 250 mg tablet for oral administration. Each tablet contains the following inactive ingredients: colloidal silicon dioxide, croscarmellose sodium, hypromellose acetate succinate, magnesium stearate, microcrystalline cellulose, and sodium lauryl sulfate. The tablet coating includes FD&C blue #2, hypromellose, lactose monohydrate, titanium dioxide, and triacetin.

12 CLINICAL PHARMACOLOGY

12.1 Mechanism of Action

Ivosidenib is a small molecule inhibitor that targets the mutant isocitrate dehydrogenase 1 (IDH1) enzyme. In patients with AML, susceptible IDH1 mutations are defined as those leading to increased levels of 2-hydroxyglutarate (2-HG) in the leukemia cells and where efficacy is predicted by 1) clinically meaningful remissions with the recommended dose of ivosidenib and/or 2) inhibition of mutant IDH1 enzymatic activity at concentrations of ivosidenib sustainable at the recommended dosage according to validated methods. The most common of such mutations in patients with AML are R132H and R132C substitutions.

Ivosidenib was shown to inhibit selected IDH1 R132 mutants at much lower concentrations than wild-type IDH1 in vitro. Inhibition of the mutant IDH1 enzyme by ivosidenib led to decreased 2-HG levels and induced myeloid differentiation in vitro and in vivo in mouse xenograft models of IDH1-mutated AML. In blood samples from patients with AML with mutated IDH1, ivosidenib decreased 2-HG levels ex-vivo, reduced blast counts, and increased percentages of mature myeloid cells.

In a patient-derived xenograft intra-hepatic cholangiocarcinoma mouse model with IDH1 R132C, ivosidenib reduced 2-HG levels.

12.2 Pharmacodynamics

Multiple doses of ivosidenib 500 mg daily were observed to decrease plasma 2-HG concentrations in patients with hematological malignancies and cholangiocarcinoma to levels similar to those observed at baseline in healthy subjects. In bone marrow of patients with hematological malignancies and in tumor biopsy of patients with cholangiocarcinoma, the mean [% coefficient of variation (%CV)] reduction in 2-HG concentrations were 93.1% (11.1%) and 82.2% (32.4%), respectively.

Cardiac Electrophysiology

The mean increase in QTc was 17 msec (UCI: 20 msec) following administration of TIBSOVO 500 mg in patients with newly diagnosed AML and patients with relapsed or refractory AML. The increase in QTc interval was concentration-dependent [see Warnings and Precautions (5.2)]. A similar mean increase following administration of TIBSOVO 500 mg daily was observed in patients with relapsed or refractory MDS and in patients with solid tumors, including patients with cholangiocarcinoma. Co-administration with moderate or strong CYP3A inhibitors is expected to further increase QTc interval prolongation from baseline.

12.3 Pharmacokinetics

The AUC and Cmax of ivosidenib increase in a less than dose-proportional manner from 200 mg to 1,200 mg daily (0.4 to 2.4 times the approved recommended dosage). The following ivosidenib pharmacokinetic parameters (Table 12) were observed following administration of ivosidenib 500 mg as a single dose or daily dose (for steady state), unless otherwise specified. The steady-state pharmacokinetics of ivosidenib 500 mg were comparable between patients with newly diagnosed AML, relapsed or refractory AML, and relapsed or refractory MDS, and were lower in patients with cholangiocarcinoma.

Table 12: Pharmacokinetics of ivosidenib
 | Newly diagnosed AML treated with a combination of TIBSOVO and azacitidine | Relapsed or refractory AML treated with TIBSOVO | Relapsed or refractory MDS treated with TIBSOVO | Cholangiocarcinoma treated with TIBSOVO
PK parameters
Single dose Cmax (ng/mL) [PK parameters expressed as mean (%CV).] | 4,820 (39%) | 4,503 (38%) | 4,020 (31%) | 4,060 (45%)
Steady state Cmax (ng/mL) | 6,145 (34%) | 6,551 (44%) | 5,820 (37%) | 4,799 (33%)
Steady state AUC (ng∙hr/mL) | 106,326 (41%) | 117,348 (50%) | 103,770 (40%) | 86,382 (34%)
Steady state PK | Within 14 days
Accumulation
Cmax | 1.2 | 1.5 | 1.4 | 1.2
AUC | 1.6 | 1.9 | 2 | 1.5
Absorption
Median Tmax (hr) | 2 | 3 | 3 | 2
Effect of Food [Following administration of a single dose in healthy subjects, a high-fat meal (approximately 900 to 1,000 calories, 500 to 600 fat calories, 250 carbohydrate calories and 150 protein calories).]
Cmax | 1.98-fold (90% CI: 1.79, 2.19)
AUC | 1.24-fold (90% CI: 1.16, 1.33)
Distribution
In vitro protein binding | 92 to 96%
Apparent volume of distribution at steady state (L) | 504 (22%) | 403 (35%) | 552 (26%) | 706 (45%)
Elimination
Apparent clearance at steady state (L/hr) | 4.6 (35%) | 5.6 (35%) | 5.1 (35%) | 6.1 (31%)
Terminal half-life at steady state (hr) | 98 (42%) | 58 (42%) | 96 (43%) | 129 (102%)
Metabolism
Plasma [Data from a single radiolabeled ivosidenib dose in healthy subjects.] | >92% of total radioactivity as ivosidenib
Metabolic pathways
Major | CYP3A4
Minor | N-dealkylation and hydrolytic pathways
Excretion
Urine | 17% (10% as unchanged ivosidenib)
Feces | 77% (67% as unchanged ivosidenib)

Specific Populations

No clinically significant effects on the pharmacokinetics of ivosidenib were observed based on age (18 years to 89 years), sex, race (White, Asian, Black or African American), body weight (38 to 150 kg), ECOG performance status, mild or moderate hepatic impairment (Child-Pugh A or B) or mild or moderate renal impairment (eGFR ≥30 mL/min/1.73m^2, MDRD). The pharmacokinetics of ivosidenib in patients with severe renal impairment (eGFR <30 mL/min/1.73m^2, MDRD) or renal impairment requiring dialysis or severe hepatic impairment (Child-Pugh C) is unknown.

Drug Interaction Studies

Clinical Studies and Model-Based Approaches

Effect of Strong or Moderate CYP3A4 Inhibitors on Ivosidenib

Co-administration of 250 mg ivosidenib with a strong CYP3A4 inhibitor (200 mg itraconazole once daily for 18 days) increased ivosidenib single-dose AUC by 269% (90% CI: 245%, 295%) with no change in Cmax in healthy subjects. Co-administration of 500 mg ivosidenib with the moderate CYP3A4 inhibitor fluconazole (dosed to steady-state) increases ivosidenib single-dose AUC by 173% with no change in Cmax. Co-administration of fluconazole following multiple daily ivosidenib doses is predicted to increase ivosidenib steady-state Cmax by 152% and AUC by 190%.

Effect of Strong CYP3A4 Inducers on Ivosidenib

Co-administration of ivosidenib with a strong CYP3A4 inducer (600 mg rifampin once daily for 15 days) is predicted to decrease ivosidenib steady-state AUC by 33%.

Effect of Ivosidenib on CYP3A4 Substrates

Ivosidenib induces CYP3A4, including its own metabolism. Co-administration of ivosidenib with CYP3A4 substrates, including certain azole anti-fungal agents, is expected to decrease CYP3A4 substrate steady-state AUC.

Effect of Gastric Acid Reducing Agents on Ivosidenib

No clinically significant ivosidenib pharmacokinetic differences were observed following co-administration with gastric acid reducing agents (e.g., proton pump inhibitors, H2-receptor antagonists, antacids).

In vitro Studies

Metabolic Pathways

Ivosidenib may induce CYP2B6, CYP2C8, and CYP2C9.

Drug Transporter Systems

Ivosidenib is a substrate for P-glycoprotein (P-gp). Ivosidenib is not a substrate for BCRP or hepatic transporters OATP1B1 and OATP1B3.

Ivosidenib is an inhibitor of OAT3 and P-gp. Ivosidenib does not inhibit BCRP, OATP1B1, OATP1B3, OAT1, and OCT2.

13 NONCLINICAL TOXICOLOGY

13.1 Carcinogenesis, Mutagenesis, Impairment of Fertility

Carcinogenicity studies have not been conducted with ivosidenib. Ivosidenib was not mutagenic in an in vitro bacterial reverse mutation (Ames) assay. Ivosidenib was not clastogenic in an in vitro human lymphocyte micronucleus assay, or in an in vivo rat bone marrow micronucleus assay. Fertility studies in animals have not been conducted with ivosidenib. In repeat-dose toxicity studies up to 90 days in duration with twice daily oral administration of ivosidenib in rats, uterine atrophy was reported in females at non-tolerated dose levels.

14 CLINICAL STUDIES

14.1 Newly Diagnosed AML

Newly Diagnosed AML in Combination with Azacitidine

The efficacy of TIBSOVO was evaluated in a randomized (1:1), multicenter, double-blind, placebo-controlled clinical trial (Study AG120-C-009, NCT03173248) of 146 adult patients with newly-diagnosed AML with an IDH1 mutation who were 75 years or older, or had comorbidities that precluded the use of intensive induction chemotherapy based on at least one of the following criteria: baseline Eastern Cooperative Oncology Group (ECOG) performance status of 2, severe cardiac or pulmonary disease, hepatic impairment with bilirubin > 1.5 times the upper limit of normal, creatinine clearance < 45 mL/min, or other comorbidity. IDH1 mutations were confirmed centrally using the Abbott RealTime™ IDH1 Assay. Local diagnostic tests were permitted for screening and randomization provided a bone marrow or peripheral blood sample was sent for central confirmation. Gene mutation analysis to document IDH1 mutated disease from a bone marrow or peripheral blood sample was conducted for all patients. Patients were randomized to receive either TIBSOVO 500 mg or matched placebo orally once daily on Days 1-28 in combination with azacitidine 75 mg/m^2/day either subcutaneously or intravenously on Days 1-7 or Days 1-5 and 8-9 of each 28-day cycle beginning on Cycle 1 Day 1. Patients were treated for a minimum of 6 cycles unless they experienced disease progression, unacceptable toxicity or undergoing hematopoietic stem cell transplantation. Baseline demographic and disease characteristics are shown in Table 13.

Table 13: Baseline Demographic and Disease Characteristics in Patients with Newly Diagnosed AML (Study AG120-C-009)
Demographic and Disease Characteristics | TIBSOVO + azacitidine (500 mg daily) N=72 | Placebo + azacitidine N=74
Demographics
Age (Years) Median (Min, Max) | 76 (58, 84) | 76 (45, 94)
Age Categories, n (%)
<65 years | 4 (6) | 4 (5)
≥65 years to <75 years | 29 (40) | 27 (36)
≥75 years | 39 (54) | 43 (58)
Sex, n (%)
Male | 42 (58) | 38 (51)
Female | 30 (42) | 36 (49)
Race, n (%)
Asian | 15 (21) | 19 (26)
White | 12 (17) | 12 (16)
Black or African American | 0 | 2 (3)
Other | 1 (1) | 1 (1)
Not provided | 44 (61) | 40 (54)
Disease Characteristics
ECOG PS, n (%)
0 | 14 (19) | 10 (14)
1 | 32 (44) | 40 (54)
2 | 26 (36) | 24 (32)
IDH1 Mutation, n (%) [Using confirmatory Abbott RealTime IDH1 assay testing results.]
R132C | 45 (63) | 51 (69)
R132H | 14 (19) | 12 (16)
R132G | 6 (8) | 4 (5)
R132L | 3 (4) | 0
R132S | 2 (3) | 6 (8)
Wild type | 1 (1) | 0
Missing | 1 (1) | 1 (1)
Cytogenetic risk status [Cytogenetic risk status: National Comprehensive Cancer Network (NCCN) guidelines.] n (%)
Favorable | 3 (4) | 7 (9)
Intermediate | 48 (67) | 44 (59)
Poor | 16 (22) | 20 (27)
Other | 3 (4) | 1 (1)
Missing | 2 (3) | 2 (3)
Transfusion Dependent at Baseline [Patients were defined as transfusion dependent at baseline if they received any red blood cell or platelet transfusion within 56 days prior to the first dose of TIBSOVO.] , n (%) | 39 (54) | 40 (54)
Type of AML, n (%)
De novo AML | 54 (75) | 53 (72)
Secondary AML | 18 (25) | 21 (28)
Therapy-related AML | 2 (3) | 1 (1)
MDS related | 10 (14) | 12 (16)
MPN related | 4 (6) | 8 (11)
ECOG PS: Eastern Cooperative Oncology Group Performance Status; MPN = Myeloproliferative Neoplasm; MDS = Myelodysplastic syndrome

Efficacy was established on the basis of event-free survival (EFS), overall survival (OS), and rate and duration of complete remission (CR). EFS was defined as the time from randomization until treatment failure, relapse from remission, or death from any cause, whichever occurred first. Treatment failure was defined as failure to achieve CR by 24 weeks. The efficacy results are shown in Table 14 and Figure 1.

Table 14: Efficacy Results in Patients with Newly Diagnosed AML (Study AG120-C-009)
Endpoint | TIBSOVO (500 mg daily) + azacitidine N=72 | Placebo + azacitidine N=74
EFS, events (%) | 47 (65) | 62 (84)
Treatment Failure | 43 (60) | 59 (80)
Relapse | 3 (4) | 2 (3)
Death | 1 (1) | 1 (1)
Hazard ratio [Hazard ratio is estimated using a Cox's proportional hazards model stratified by the randomization stratification factors (AML status and geographic region) with Placebo+ azacitidine as the denominator.] (95% CI) | 0.35 (0.17, 0.72)
p-value [Two-sided p-value is calculated from the log-rank test stratified by the randomization stratification factors (AML status and geographic region).] | 0.0038
OS events (%) | 28 (39) | 46 (62)
Median OS (95% CI) months | 24.0 (11.3, 34.1) | 7.9 (4.1, 11.3)
Hazard ratio (95% CI) | 0.44 (0.27, 0.73)
p-value | 0.0010
CR, n (%) | 34 (47) | 11 (15)
95% CI [CI of percentage is calculated with the Clopper and Pearson (exact Binomial) method.] | (35, 59) | (8, 25)
Risk difference [Mantel-Haenszel estimate of risk difference in percentage between TIBSOVO + azacitidine and Placebo+ azacitidine is calculated.] (95% CI), (%) | 31 (17, 46)
p-value [Two-sided p-value is calculated from the Cochran-Mantel-Haenszel test stratified by the randomization stratification factors (AML status and geographic region).] | <0.0001
Median duration of CR (95% CI), months | NE (13.0, NE) | 11.2 (3.2, NE)
CR +CRh, n (%) | 37 (51) | 13 (18)
95% CI | (39, 63) | (10, 28)
Risk difference (95% CI), (%) | 33 (18, 47)
p-value | <0.0001
Median duration of CR + CRh (95% CI), months | NE (13.0, NE) | 9.2 (5.8, NE)
Abbreviations: EFS = Event free survival; CI: confidence interval; OS = Overall survival; CR = Complete remission; CRh = Complete remission with partial hematologic recovery; NE = Not estimable.
The 2-sided p-value boundaries for EFS, OS, CR, and CR+CRh are 0.0095, 0.0034, 0.0174, and 0.0174, respectively.

Figure 1: Kaplan-Meier Curve for Overall Survival in AG120-C-009

The median time to first CR for TIBSOVO with azacitidine was 4 months (range, 1.7 to 11.9 months).

The median time to first CR + CRh for TIBSOVO with azacitidine was 4 months (range, 1.7 to 11.9 months).

Monotherapy in Newly Diagnosed AML

The efficacy of TIBSOVO was evaluated in an open-label, single-arm, multicenter clinical trial (Study AG120-C-001, NCT02074839) that included 28 adult patients with newly diagnosed AML with an IDH1 mutation. IDH1 mutations were identified by a local or central diagnostic test and confirmed retrospectively using the Abbott RealTime™ IDH1 Assay. The cohort included patients who were age 75 years or older or who had comorbidities that precluded the use of intensive induction chemotherapy based on at least one of the following criteria: baseline ECOG performance status of ≥ 2, severe cardiac or pulmonary disease, hepatic impairment with bilirubin > 1.5 times the upper limit of normal, or creatinine clearance < 45 mL/min. TIBSOVO was given orally at a starting dose of 500 mg daily until disease progression, development of unacceptable toxicity, or undergoing hematopoietic stem cell transplantation. Two (7%) of the 28 patients went on to stem cell transplantation following TIBSOVO treatment.

The baseline demographic and disease characteristics are shown in Table 15.

Table 15: Baseline Demographic and Disease Characteristics in Patients with Newly Diagnosed AML (Study AG120-C-001)
Demographic and Disease Characteristics | TIBSOVO (500 mg daily) N=28
Demographics
Age (Years) Median (Min, Max) | 77 (64, 87)
Age Categories, n (%)
<65 years | 1 (4)
≥65 years to <75 years | 8 (29)
≥75 years | 19 (68)
Sex, n (%)
Male | 15 (54)
Female | 13 (46)
Race, n (%)
White | 24 (86)
Black or African American | 2 (7)
Asian | 0
Native Hawaiian/Other Pacific Islander | 0
Other/Not provided | 2 (7)
Disease Characteristics
ECOG PS, n (%)
0 | 6 (21)
1 | 16 (57)
2 | 5 (18)
3 | 1 (4)
IDH1 Mutation, n (%) [Using confirmatory Abbott RealTime IDH1 assay testing results.]
R132C | 24 (86)
R132H | 2 (7)
R132G | 1 (4)
R132L | 1 (4)
R132S | 0
ELN Risk Category, n (%)
Favorable | 0
Intermediate | 9 (32)
Adverse | 19 (68)
Transfusion Dependent at Baseline [Patients were defined as transfusion dependent at baseline if they received any transfusion occurring within 56 days prior to the first dose of TIBSOVO.] , n (%) | 17 (61)
Type of AML, n (%)
De novo AML | 6 (21)
AML-MRC [AML with myelodysplasia-related changes.] | 19 (68)
Therapy-related AML | 3 (11)
Prior Hypomethylating Agent for Antecedent
Hematologic Disorder | 13 (46)
ECOG PS: Eastern Cooperative Oncology Group Performance Status. ELN: European Leukemia Net

Efficacy was established on the basis of the rate of complete remission (CR) or complete remission with partial hematologic recovery (CRh), the duration of CR+CRh, and the rate of conversion from transfusion dependence to transfusion independence. The efficacy results are shown in Table 16. The median follow-up was 8.1 months (range, 0.6 to 40.9 months) and median treatment duration was 4.3 months (range, 0.3 to 40.9 months).

Table 16: Efficacy Results in Patients with Newly Diagnosed AML (Study AG120-C-001)
Endpoint | TIBSOVO (500 mg daily) N=28
CR [CR (complete remission) was defined as <5% blasts in the bone marrow, no evidence of disease, and full recovery of peripheral blood counts (platelets >100,000/microliter and absolute neutrophil counts [ANC] >1,000/microliter).] n (%) | 8 (28.6)
95% CI | (13.2, 48.7)
Median DOCR [DOCR (duration of CR), DOCRh (duration of CRh), and DOCR+CRh (duration of CR+CRh) was defined as time since first response of CR, CRh or CR/CRh, respectively, to relapse or death, whichever is earlier. + indicates censored observation.] (months) | NE [The median durations of CR and CR+CRh were not estimable, with 5 patients (41.7%) who achieved CR or CRh remaining on TIBSOVO treatment (treatment duration range: 20.3 to 40.9 months).]
95% CI | (4.2, NE)
CRh [CRh (complete remission with partial hematological recovery) was defined as <5% blasts in the bone marrow, no evidence of disease, and partial recovery of peripheral blood counts (platelets >50,000/microliter and ANC >500/microliter).] n (%) | 4 (14.3)
95% CI | (4.0, 32.7)
Observed DOCRh (months) | 2.8, 4.6, 8.3, 15.7+
CR+CRh n (%) | 12 (42.9)
95% CI | (24.5, 62.8)
Median DOCR+CRh (months) | NE
95% CI | (4.2, NE)
CI: confidence interval, NE: not estimable

For patients who achieved a CR or CRh, the median time to CR or CRh was 2.8 months (range, 1.9 to 12.9 months). Of the 12 patients who achieved a best response of CR or CRh, 11 (92%) achieved a first response of CR or CRh within 6 months of initiating TIBSOVO.

Among the 17 patients who were dependent on red blood cell (RBC) and/or platelet transfusions at baseline, 7 (41.2%) became independent of RBC and platelet transfusions during any 56-day post-baseline period. Of the 11 patients who were independent of both RBC and platelet transfusions at baseline, 6 (54.5%) remained transfusion independent during any 56-day post-baseline period.

14.2 Relapsed or Refractory AML

The efficacy of TIBSOVO was evaluated in an open-label, single-arm, multicenter clinical trial (Study AG120-C-001, NCT02074839) of 174 adult patients with relapsed or refractory AML with an IDH1 mutation. IDH1 mutations were identified by a local or central diagnostic test and confirmed retrospectively using the Abbott RealTime™ IDH1 Assay. TIBSOVO was given orally at a starting dose of 500 mg daily until disease progression, development of unacceptable toxicity, or undergoing hematopoietic stem cell transplantation. Twenty-one (12%) of the 174 patients went on to stem cell transplantation following TIBSOVO treatment.

The baseline demographic and disease characteristics are shown in Table 17.

Table 17: Baseline Demographic and Disease Characteristics in Patients with Relapsed or Refractory AML (Study AG120-C-001)
Demographic and Disease Characteristics | TIBSOVO (500 mg daily) N=174
Demographics
Age (Years) Median (Min, Max) | 67 (18, 87)
Age Categories, n (%)
<65 years | 63 (36)
≥65 years to <75 years | 71 (41)
≥75 years | 40 (23)
Sex, n (%)
Male | 88 (51)
Female | 86 (49)
Race, n (%)
White | 108 (62)
Black or African American | 10 (6)
Asian | 6 (3)
Native Hawaiian/Other Pacific Islander | 1 (1)
Other/Not provided | 49 (28)
Disease Characteristics
ECOG PS, n (%)
0 | 36 (21)
1 | 97 (56)
2 | 39 (22)
3 | 2 (1)
IDH1 Mutation, n (%) [Using confirmatory Abbott RealTime IDH1 assay testing results.]
R132C | 102 (59)
R132H | 43 (25)
R132G | 12 (7)
R132S | 10 (6)
R132L | 7 (4)
Cytogenetic Risk Status, n (%)
Intermediate | 104 (60)
Poor | 47 (27)
Missing/Unknown | 23 (13)
Relapse Type
Primary refractory | 64 (37)
Refractory relapse | 45 (26)
Untreated relapse | 65 (37)
Relapse Number
0 | 64 (37)
1 | 83 (48)
2 | 21 (12)
≥3 | 6 (3)
Prior Stem Cell Transplantation for AML, n (%) | 40 (23)
Transfusion Dependent at Baseline [Patients were defined as transfusion dependent at baseline if they received any transfusion occurring within 56 days prior to the first dose of TIBSOVO.] , n (%) | 110 (63)
Median Number of Prior Therapies (Min, Max) | 2 (1, 6)
Type of AML, n (%)
De novo AML | 116 (67)
Secondary AML | 58 (33)
ECOG PS: Eastern Cooperative Oncology Group Performance Status.

Efficacy was established on the basis of the rate of complete remission (CR) plus complete remission with partial hematologic recovery (CRh), the duration of CR+CRh, and the rate of conversion from transfusion dependence to transfusion independence. The efficacy results are shown in Table 18. The median follow-up was 8.3 months (range, 0.2 to 39.5 months) and median treatment duration was 4.1 months (range, 0.1 to 39.5 months).

Table 18: Efficacy Results in Patients with Relapsed or Refractory AML (Study AG120-C-001)
Endpoint | TIBSOVO (500 mg daily) N=174
CR [CR (complete remission) was defined as <5% blasts in the bone marrow, no evidence of disease, and full recovery of peripheral blood counts (platelets >100,000/microliter and absolute neutrophil counts [ANC] >1,000/microliter).] n (%) | 43 (24.7)
95% CI | (18.5, 31.8)
Median DOCR [DOCR (duration of CR), DOCRh (duration of CRh), and DOCR+CRh (duration of CR+CRh) was defined as time since first response of CR, CRh or CR/CRh, respectively, to relapse or death, whichever is earlier.] (months) | 10.1
95% CI | (6.5, 22.2)
CRh [CRh (complete remission with partial hematological recovery) was defined as <5% blasts in the bone marrow, no evidence of disease, and partial recovery of peripheral blood counts (platelets >50,000/microliter and ANC >500/microliter).] n (%) | 14 (8.0)
95% CI | (4.5, 13.1)
Median DOCRh (months) | 3.6
95% CI | (1, 5.5)
CR+CRh [CR+CRh rate appeared to be consistent across all baseline demographic and baseline disease characteristics with the exception of number of prior regimens.] n (%) | 57 (32.8)
95% CI | (25.8, 40.3)
Median DOCR+CRh (months) | 8.2
95% CI | (5.6, 12)
CI: confidence interval

For patients who achieved a CR or CRh, the median time to CR or CRh was 2 months (range, 0.9 to 5.6 months). Of the 57 patients who achieved a best response of CR or CRh, all achieved a first response of CR or CRh within 6 months of initiating TIBSOVO.

Among the 110 patients who were dependent on red blood cell (RBC) and/or platelet transfusions at baseline, 41 (37.3%) became independent of RBC and platelet transfusions during any 56-day post-baseline period. Of the 64 patients who were independent of both RBC and platelet transfusions at baseline, 38 (59.4%) remained transfusion independent during any 56-day post-baseline period.

14.3 Relapsed or Refractory MDS

The efficacy of TIBSOVO was evaluated in an open-label, single-arm, multicenter study (study AG120-C-001, NCT02074839) of 18 adult patients with relapsed or refractory MDS with an IDH1 mutation. IDH1 mutations were detected in peripheral blood or bone marrow by a local or central diagnostic test and confirmed retrospectively using the Abbott RealTime™ IDH1 Assay. TIBSOVO was given orally at a starting dose of 500 mg daily continuous for 28-day cycles until disease progression, development of unacceptable toxicity, or undergoing hematopoietic stem cell transplantation. One (6%) of the 18 patients went on to stem cell transplantation following TIBSOVO treatment.

The baseline demographic and disease characteristics are shown in Table 19.

Table 19: Baseline Demographic and Disease Characteristics in Patients with Relapsed or Refractory MDS (Study AG120-C-001)
Demographic and Disease Characteristics | TIBSOVO (500 mg daily) N=18
Demographics
Age (Years) Median (Min, Max) | 74 (61, 82)
Age Categories, n (%)
<65 years | 3 (17)
≥65 years to <75 years | 7 (39)
≥75 years | 8 (44)
Sex, n (%)
Male | 14 (78)
Female | 4 (22)
Race, n (%)
White | 14 (78)
Black or African American | 1 (6)
Not Reported | 3 (17)
Disease Characteristics
ECOG PS, n (%)
0 | 5 (28)
1 | 10 (56)
2 | 3 (17)
IDH1 Mutation, n (%) [Using confirmatory Abbott RealTime IDH1 assay testing results.]
R132C | 9 (50)
R132H | 5 (28)
R132G | 2 (11)
R132L | 1 (6)
R132S | 1 (6)
Cytogenetic Risk Status, n (%)
Good | 4 (22)
Intermediate | 8 (44)
Poor | 5 (28)
Missing | 1 (6)
Baseline Bone Marrow Blasts, n (%)
< 5% | 7 (39)
≥ 5% | 11 (61)
Prior Therapies
Intensive chemotherapy | 3 (17)
Non-intensive chemotherapy | 15 (83)
1 line of HMA-based therapy | 14 (78)
2 lines of HMA-based therapy | 1 (6)
ECOG PS: Eastern Cooperative Oncology Group Performance Status.

Efficacy was established on the basis of the rate of complete remission (CR) or partial remission (PR) as per the 2006 International Working Group response criteria for MDS, the duration of CR+PR, and the rate of conversion from transfusion dependence to transfusion independence. All observed responses were CRs. The efficacy results are shown in Table 20. The median follow-up was 27.1 months (range 3.7 to 88.7 months) and median duration of exposure to TIBSOVO was 8.3 months (range 3.3 to 78.8 months).

Table 20: Efficacy Results in Patients with Relapsed or Refractory MDS (Study AG120-C-001)
Endpoint | TIBSOVO (500 mg daily) N=18
CR [CR responders with baseline bone marrow blast < 5% was 43% (3/7).] n (%) | 7 (38.9)
95% CI | (17.3, 64.3)
DOCR [Duration of CR (DOCR) = date of first documented CR (lasted at least 4 weeks) to date of first documented confirmed relapse or death, whichever is earlier.] (months) median (range) | NE (1.9, 80.8+ [+ indicates censored observation.])
CI: confidence interval, CR: complete remission, NE: not estimable, derived based on Kaplan-Meier method.

For patients who achieved a CR, the median time to CR was 1.9 months (range, 1.0 to 5.6 months).

Among the 9 patients who were dependent on red blood cell (RBC) and/or platelet transfusions at baseline, 6 (67%) became independent of RBC and platelet transfusions during any 56-day post-baseline period. Of the 9 patients who were independent of both RBC and platelet transfusions at baseline, 7 (78%) remained transfusion independent during any 56-day post-baseline period.

14.4 Locally Advanced or Metastatic Cholangiocarcinoma

The efficacy of TIBSOVO was evaluated in a randomized (2:1), multicenter, double-blind, placebo-controlled clinical trial (Study AG120-C-005, NCT02989857) of 185 adult patients with locally advanced or metastatic cholangiocarcinoma with an IDH1 mutation whose disease had progressed following at least 1 but not more than 2 prior regimens, including at least one gemcitabine- or 5-FU-containing regimen. Patients were randomized to receive either TIBSOVO 500 mg orally once daily or matched placebo until disease progression or unacceptable toxicity. Randomization was stratified by number of prior therapies (1 or 2). Eligible patients who were randomized to placebo were allowed to cross over to receive TIBSOVO after documented radiographic disease progression. Patients with IDH1 mutations were selected using a central diagnostic next generation sequencing assay. Tumor imaging assessments were performed every 6 weeks for the first 8 assessments and every 8 weeks thereafter.

The major efficacy outcome measure was Progression Free Survival (PFS) as determined by independent review committee (IRC) according to Response Evaluation Criteria in Solid Tumors (RECIST) v1.1.

The median age was 62 years (range: 33 to 83); 63% were female; 57% were White, 12% Asian, 1.1% Black, 0.5% Native Hawaiian/Other Pacific Islander, 0.5% American Indian or Alaska Native, 28% race missing/not reported; and 37% had an ECOG performance status of 0 (37%) or 1 (62%). All patients received at least 1 prior line of systemic therapy and 47% received two prior lines. Most patients had intrahepatic cholangiocarcinoma (91%) at diagnosis and 92% had metastatic disease. Across both arms, 70% patients had an R132C mutation, 15% had an R132L mutation, 12% had an R132G mutation, 1.1% had an R132H mutation, and 1.6% had an R132S mutation.

The efficacy results are shown in Table 21 and Figure 2. The study demonstrated a statistically significant improvement in PFS.

Table 21: Efficacy Results in Patients with Locally Advanced or Metastatic Cholangiocarcinoma in AG120-C-005
Endpoint | TIBSOVO (500 mg daily) | Placebo
Progression-Free Survival by IRC Assessment | N=124 | N=61
Events, n (%) | 76 (61) | 50 (82)
Progressive Disease | 64 (52) | 44 (72)
Death | 12 (10) | 6 (10)
Hazard ratio (95% CI) [Hazard ratio is calculated from stratified Cox regression model. Stratified by number of prior lines of therapy.] | 0.37 (0.25, 0.54)
p-value [P-value is calculated from the one-sided stratified log-rank test. Stratified by number of prior lines of therapy.] | <0.0001
Objective Response Rate, n (%) | 3 (2.4) | 0
Overall Survival [OS results are based on the final analysis of OS (based on 150 deaths) which occurred 16 months after the final analysis of PFS. The median OS (95% CI) for TIBSOVO was 10.3 (7.8, 12.4) months; and placebo was 7.5 (4.8, 11.1) months without adjusting for crossover. In the analysis of OS, 70% of the patients randomized to placebo had crossed over to receive TIBSOVO after radiographic disease progression.] | N=126 | N=61
Deaths, n (%) | 100 (79) | 50 (82)
Hazard ratio (95% CI) | 0.79 (0.56, 1.12)
p-value | 0.093
IRC: Independent Review Committee; CI: Confidence Interval

Figure 2: Kaplan-Meier Plot of Progression-Free Survival per Independent Review Committee - Before Crossover (ITT)

16 HOW SUPPLIED/STORAGE AND HANDLING

How Supplied

250 mg tablet: Blue oval-shaped film-coated tablet debossed "IVO" on one side and "250" on the other side.

- 60-count bottles of 250 mg tablets with a desiccant canister (NDC 72694-617-60)

Storage

Store at 20°C to 25°C (68°F to 77°F); excursions permitted between 15°C to 30°C (59°F to 86°F) [see USP Controlled Room Temperature].

17 PATIENT COUNSELING INFORMATION

Advise the patient to read the FDA-approved patient labeling (Medication Guide).

Differentiation Syndrome in AML and MDS

Advise patients being treated with TIBSOVO of the risks of developing differentiation syndrome as early as 1 day after start of therapy and during the first 3 months on treatment. Ask patients to immediately report any symptoms suggestive of differentiation syndrome, such as fever, cough or difficulty breathing, rash, decreased urinary output, low blood pressure, rapid weight gain, or swelling of their arms or legs, to their healthcare provider for further evaluation [see Boxed Warning and Warnings and Precautions (5.1)].

QTc Interval Prolongation

Inform patients of symptoms that may be indicative of significant QTc interval prolongation including dizziness, lightheadedness, and fainting. Advise patients to report these symptoms and the use of all medications to their healthcare provider [see Warnings and Precautions (5.2)].

Guillain-Barré Syndrome

Inform patients of symptoms that may be indicative of Guillain-Barré syndrome, including new signs or symptoms of motor and/or sensory neuropathy, such as weakness or tingling sensation in the legs, arms, or upper body, numbness and pain on one side or both sides of the body, changes to any sensory function, or burning or prickling sensation, or difficulty breathing. Advise patients to report these symptoms to their healthcare provider [see Warnings and Precautions (5.3)].

Drug Interactions

Advise patients to inform their healthcare providers of all concomitant medications, including over-the-counter medications, vitamins, and herbal products [see Drug Interactions (7)].

Tumor Lysis Syndrome

Advise patients on the risks of developing tumor lysis syndrome. Advise patients on the importance of maintaining high fluid intake, and the need for frequent monitoring of blood chemistry values [see Adverse Reactions (6.1)].

Gastrointestinal Adverse Reactions

Advise patients on the risks of experiencing gastrointestinal reactions such as diarrhea, nausea, mucositis, constipation, vomiting, decreased appetite, ascites and abdominal pain. Ask patients to report these events to their healthcare provider and advise patients how to manage them [see Adverse Reactions (6.1)].

Lactation

Advise women not to breastfeed during treatment with TIBSOVO and for 1 month after the last dose [see Use in Specific Populations (8.2)].

Dosing and Storage Instructions

- Advise patients to swallow tablets whole and to not split, crush, or chew TIBSOVO tablets.
- Advise patients to avoid taking TIBSOVO with a high-fat meal.
- Instruct patients that if a dose of TIBSOVO is vomited, not to take an additional dose, and wait until the next scheduled dose is due. If a dose of TIBSOVO is missed or not taken at the usual time, instruct patients to take the dose as soon as possible unless the next dose is due within 12 hours. Patients can return to the normal schedule the following day.
- Store TIBSOVO at room temperature from 20°C to 25°C (68°F to 77°F).
- Advise patients not to remove the desiccant canister from the bottle.

Manufactured for Servier Pharmaceuticals LLC, Boston, MA 02210

Servier and the Servier logo are registered trademarks of Les Laboratoires Servier.

TIBSOVO is a registered trademark of Servier Pharmaceuticals LLC, a wholly owned, indirect subsidiary of Les Laboratoires Servier.

© 2023 Servier Pharmaceuticals LLC
AG-PI-006

MEDICATION GUIDE
TIBSOVO® (tib-SOH-voh)
(ivosidenib) tablets

What is the most important information I should know about TIBSOVO?

TIBSOVO may cause serious side effects, including:

- Differentiation Syndrome. Differentiation syndrome is a common condition that affects your blood cells and may be life-threatening or lead to death. Differentiation syndrome in adults with acute myeloid leukemia (AML) and myelodysplastic syndromes (MDS) has happened as early as 1 day and up to 3 months after starting TIBSOVO. Call your healthcare provider or go to the nearest hospital emergency room right away if you develop any of the following symptoms of differentiation syndrome during treatment with TIBSOVO:

- fever
- cough
- trouble breathing
- rash

- decreased urination
- dizziness or lightheadedness
- rapid weight gain
- swelling of your arms or legs

If you develop signs and symptoms of differentiation syndrome, your healthcare provider may treat you with a corticosteroid medicine or a medicine called hydroxyurea and may monitor you in the hospital.

See "What are the possible side effects of TIBSOVO?" for more information about side effects.

What is TIBSOVO?

TIBSOVO is a prescription medicine used to treat adults with an isocitrate dehydrogenase-1 (IDH1) mutation with:

- acute myeloid leukemia (AML):
  - with newly diagnosed AML treated in combination with azacitidine, or alone, who are 75 years or older or who have health problems that prevent the use of certain chemotherapy treatments.
  - when the disease has come back or has not improved after previous treatment(s).
- myelodysplastic syndrome (MDS):
  - when the disease has come back or has not improved after previous treatment(s).
- bile duct cancer (cholangiocarcinoma):
  - with bile duct cancer that has spread and
  - who have already received previous treatment(s).

Your healthcare provider will perform a test to make sure that TIBSOVO is right for you.

It is not known if TIBSOVO is safe and effective in children.

Before taking TIBSOVO, tell your healthcare provider about all of your medical conditions, including if you:

- have any heart problems, including a condition called long QT syndrome.
- have problems with abnormal electrolytes, such as sodium, potassium, calcium or magnesium levels.
- have nervous system problems.
- have problems with your kidneys or are on dialysis.
- have any liver disorders, including cirrhosis.
- are pregnant or plan to become pregnant. TIBSOVO may cause harm to your unborn baby. You should avoid becoming pregnant during treatment with TIBSOVO. Tell your healthcare provider right away if you become pregnant or think you might be pregnant during treatment with TIBSOVO.
- are breastfeeding or plan to breastfeed. It is not known if TIBSOVO passes into your breast milk. Do not breastfeed during your treatment with TIBSOVO and for 1 month after your last dose of TIBSOVO.

Tell your healthcare provider about all the medicines you take, including prescription and over-the-counter medicines, vitamins, and herbal supplements.

Especially tell your healthcare provider if you take hormonal contraceptives. TIBSOVO may affect how hormonal contraceptives work and may cause them to not work as well.

How should I take TIBSOVO?

- Take TIBSOVO exactly as your healthcare provider tells you to.
- Do not change your dose or stop taking TIBSOVO without talking to your healthcare provider.
- Take TIBSOVO 1 time a day about the same time each day.
- Swallow TIBSOVO tablets whole. Do not split, crush, or chew the tablet.
- TIBSOVO can be taken with or without food.
- Do not take TIBSOVO with a high-fat meal. An example of a high-fat meal includes 2 eggs fried in butter, 2 strips of bacon, 2 slices of white bread with butter, 1 croissant with 1 slice of cheese, and 8 ounces of whole milk (approximately 1,000 calories and 58 grams of fat).
- If you vomit after taking a dose of TIBSOVO, do not take an additional dose. Take your next dose at your usual time.
- If you miss a dose of TIBSOVO or did not take it at the usual time, take your dose as soon as possible and at least 12 hours before your next dose. Return to your normal schedule the following day. Do not take 2 doses of TIBSOVO within 12 hours.

What are the possible side effects of TIBSOVO?

TIBSOVO may cause serious side effects, including:

- See "What is the most important information I should know about TIBSOVO?"
- Changes in the electrical activity of your heart called QTc prolongation. QTc prolongation can cause irregular heartbeats that can be life-threatening. Your healthcare provider will check the electrical activity of your heart with a test called an electrocardiogram (ECG) before and during treatment with TIBSOVO. Tell your healthcare provider right away if you feel dizzy, lightheaded, or faint.
- Guillain-Barré syndrome has happened in people treated with TIBSOVO. Your healthcare provider will monitor you for nervous system problems and will permanently stop your treatment with TIBSOVO if you develop Guillain-Barré syndrome. Tell your healthcare provider right away if you develop any signs or symptoms of Guillain-Barré syndrome, including:

- weakness or tingling feeling in your legs, arms, or upper body
- numbness and pain on one side or both sides of your body

- any changes in your ability to see, touch, hear, or taste
- burning or prickling sensation
- difficulty breathing

The most common side effects of TIBSOVO when used in combination with azacitidine or alone in adults with AML include:

- changes in certain blood cell counts
- diarrhea
- increased blood sugar
- fatigue
- changes in certain liver function tests
- swelling of arms or legs
- decreased levels of electrolytes in the blood
- nausea
- vomiting
- decreased appetite
- joint pain

- shortness of breath
- uric acid increased
- stomach (abdominal) pain
- changes in certain kidney function tests
- pain or sores in your mouth or throat
- rash
- irregular heart rhythm or heartbeat (QTc prolongation)
- differentiation syndrome
- muscle pain

The most common side effects of TIBSOVO when used in adults with Myelodysplastic Syndromes (MDS) include:

- changes in certain kidney function tests
- changes in certain blood cell counts
- joint pain, back pain, or neck pain
- decreased levels of albumin in the blood
- changes in liver function tests
- fatigue
- diarrhea
- cough

- decreased levels of sodium in the blood
- pain or sores in your mouth or throat
- decreased appetite
- muscle pain
- decreased levels of phosphorus in the blood
- itchy skin
- rash

The most common side effects of TIBSOVO in adults with Cholangiocarcinoma include:

- fatigue
- nausea
- abdominal pain
- diarrhea
- cough
- decreased appetite

- fluid and swelling in your stomach area
- vomiting
- hemoglobin decreased (anemia)
- rash
- changes in liver function tests

Your healthcare provider will do blood tests before you start and during treatment with TIBSOVO. Your healthcare provider may decrease, temporarily hold, or permanently stop your treatment with TIBSOVO if you develop certain side effects.

TIBSOVO may cause fertility problems in females and males, which may affect your ability to have children. Talk to your healthcare provider if you have concerns about fertility. These are not all of the possible side effects of TIBSOVO.

Call your doctor for medical advice about side effects. You may report side effects to FDA at 1-800-FDA-1088.

How should I store TIBSOVO?

- Store TIBSOVO at room temperature between 68°F to 77°F (20°C to 25°C).
- Do not remove the desiccant canister from the bottle.

Keep TIBSOVO and all medicines out of the reach of children.

General information about the safe and effective use of TIBSOVO

Medicines are sometimes prescribed for purposes other than those listed in a Medication Guide. Do not take TIBSOVO for conditions for which it was not prescribed. Do not give TIBSOVO to other people, even if they have the same symptoms you have. It may harm them. You can ask your pharmacist or healthcare provider for information about TIBSOVO that is written for healthcare professionals.

What are the ingredients in TIBSOVO?

Active ingredient: ivosidenib

Inactive ingredients: colloidal silicon dioxide, croscarmellose sodium, hypromellose acetate succinate, magnesium stearate, microcrystalline cellulose, and sodium lauryl sulfate. The tablet coating includes FD&C blue #2, hypromellose, lactose monohydrate, titanium dioxide, and triacetin.

Manufactured for Servier Pharmaceuticals LLC, Boston, MA 02210

Servier and the Servier logo are registered trademarks of Les Laboratoires Servier. TIBSOVO is a registered trademark of Servier Pharmaceuticals LLC, a wholly owned, indirect subsidiary of Les Laboratoires Servier.

© 2023 Servier Pharmaceuticals LLC

For more information go to www.TIBSOVO.com or call 1-800-807-6124.

AG-MG-006

This Medication Guide has been approved by the U.S. Food and Drug Administration.

Revised: OCT 2023

PRINCIPAL DISPLAY PANEL - 250 mg Tablet Bottle Carton

NDC 72694-617-60

TIBSOVO®
(ivosidenib tablets)

250 mg

Dispense the enclosed
Medication Guide to each patient

Swallow tablets whole. Do not split,
crush, or chew the tablet.

1 Bottle containing 60 tablets

Rx only